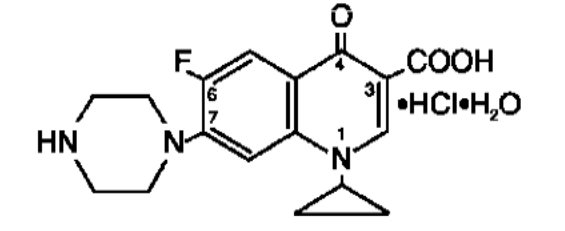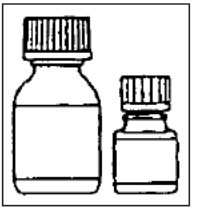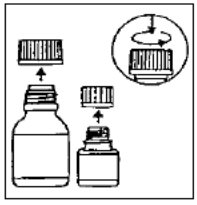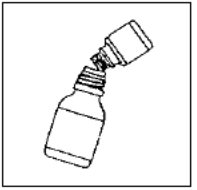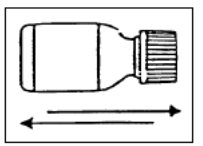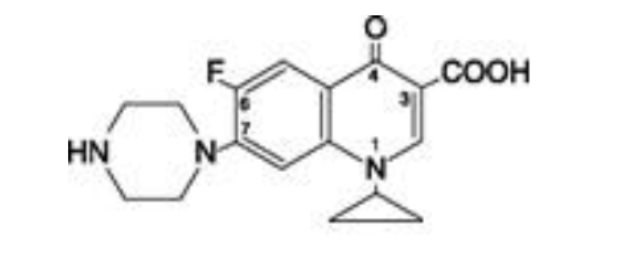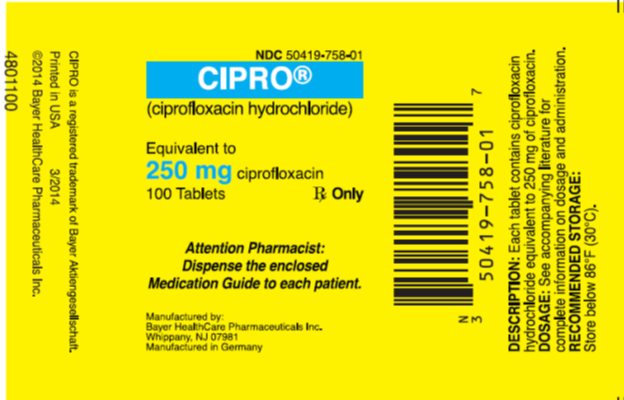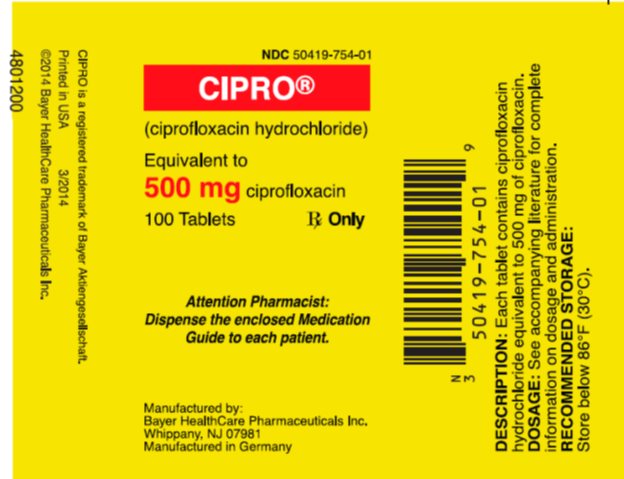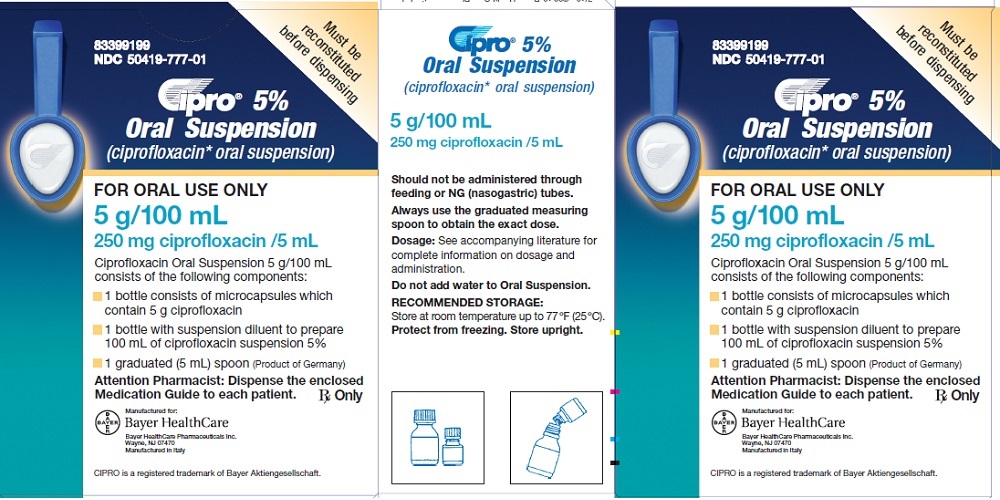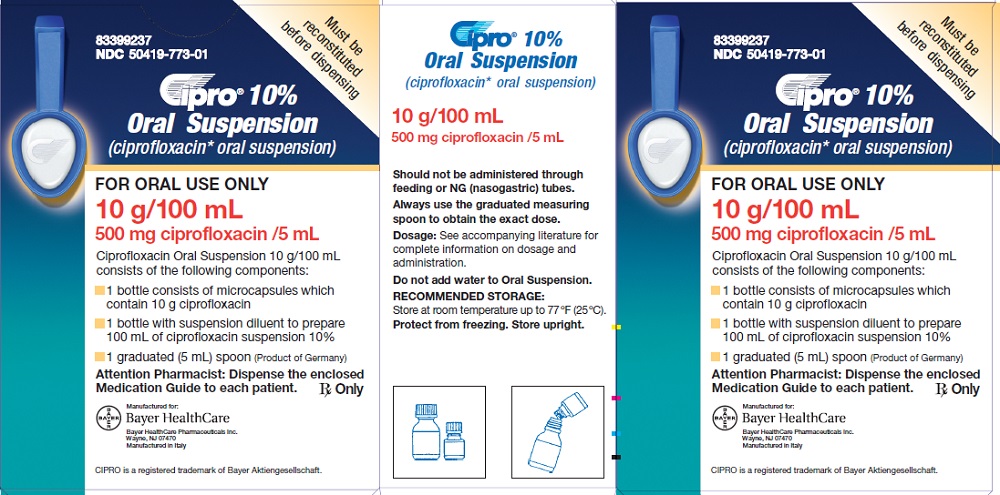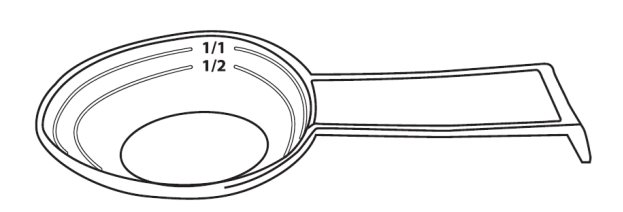 DRUG LABEL: Cipro
NDC: 50419-758 | Form: TABLET, FILM COATED
Manufacturer: Bayer HealthCare Pharmaceuticals Inc.
Category: prescription | Type: HUMAN PRESCRIPTION DRUG LABEL
Date: 20240920

ACTIVE INGREDIENTS: CIPROFLOXACIN HYDROCHLORIDE 250 mg/1 1
INACTIVE INGREDIENTS: STARCH, CORN; MICROCRYSTALLINE CELLULOSE; SILICON DIOXIDE; CROSPOVIDONE (120 .MU.M); MAGNESIUM STEARATE; HYPROMELLOSE, UNSPECIFIED; TITANIUM DIOXIDE; POLYETHYLENE GLYCOL, UNSPECIFIED

HIGHLIGHTS OF PRESCRIBING INFORMATION

These highlights do not include all the information needed to use CIPRO safely and effectively. See full prescribing information for CIPRO.
CIPRO® (ciprofloxacin hydrochloride) tablet, for oral use
CIPRO® (ciprofloxacin), for oral suspension
Initial U.S. Approval: 1987

RECENT MAJOR CHANGES

Warnings and Precautions, Hypersensitivity Reactions (5.7) 9/2024

WARNING: SERIOUS ADVERSE REACTIONS INCLUDING TENDINITIS, TENDON RUPTURE, PERIPHERAL NEUROPATHY, CENTRAL NERVOUS SYSTEM EFFECTS AND EXACERBATION OF MYASTHENIA GRAVIS

See full prescribing information for complete boxed warning.

- Fluoroquinolones, including CIPRO®, have been associated with disabling and potentially irreversible serious adverse reactions that have occurred together (5.1), including:
  - Tendinitis and tendon rupture (5.2)
  - Peripheral neuropathy (5.3)
  - Central nervous system effects (5.4)
Discontinue CIPRO immediately and avoid the use of fluoroquinolones, including CIPRO, in patients who experience any of these serious adverse reactions (5.1)
- Fluoroquinolones, including CIPRO, may exacerbate muscle weakness in patients with myasthenia gravis. Avoid CIPRO in patients with known history of myasthenia gravis. (5.5)
- Because fluoroquinolones, including CIPRO, have been associated with serious adverse reactions (5.1-5.16), reserve CIPRO for use in patients who have no alternative treatment options for the following indications:
  - Acute exacerbation of chronic bronchitis (1.10)
  - Acute uncomplicated cystitis (1.11)

Acute sinusitis (1.12)

1 INDICATIONS AND USAGE

CIPRO is a fluoroquinolone antibacterial indicated in adults (18 years of age and older) with the following infections caused by designated, susceptible bacteria and in pediatric patients where indicated:

- Skin and Skin Structure Infections (1.1)
- Bone and Joint Infections (1.2)
- Complicated Intra-Abdominal Infections (1.3)
- Infectious Diarrhea (1.4)
- Typhoid Fever (Enteric Fever) (1.5)
- Uncomplicated Cervical and Urethral Gonorrhea (1.6)
- Inhalational Anthrax post-exposure in adult and pediatric patients (1.7)
- Plague in adult and pediatric patients (1.8)
- Chronic Bacterial Prostatitis (1.9)
- Lower Respiratory Tract Infections (1.10)
  - Acute Exacerbation of Chronic Bronchitis
- Urinary Tract Infections (1.11)
  - Urinary Tract Infections (UTI)
  - Acute Uncomplicated Cystitis
  - Complicated UTI and Pyelonephritis in Pediatric Patients
- Acute Sinusitis (1.12)

Usage

To reduce the development of drug-resistant bacteria and maintain the effectiveness of CIPRO and other antibacterial drugs, CIPRO should be used only to treat or prevent infections that are proven or strongly suspected to be caused by bacteria. (1.13)

2 DOSAGE AND ADMINISTRATION

Adult Dosage Guidelines
Infection | Dose | Frequency | Duration
Skin and Skin Structure | 500 -750 mg | every 12 hours | 7 to 14 days
Bone and Joint | 500-750 mg | every 12 hours | 4 to 8 weeks
Complicated Intra-Abdominal | 500 mg | every 12 hours | 7 to 14 days
Infectious Diarrhea | 500 mg | every 12 hours | 5 to 7 days
Typhoid Fever | 500 mg | every 12 hours | 10 days
Uncomplicated Gonorrhea | 250 mg | single dose | single dose
Inhalational anthrax (post-exposure) | 500 mg | every 12 hours | 60 days
Plague | 500–750 mg | every 12 hours | 14 days
Chronic Bacterial Prostatitis | 500 mg | every 12 hours | 28 days
Lower Respiratory Tract | 500 -750 mg | every 12 hours | 7 to 14 days
Urinary Tract | 250-500 mg | every 12 hours | 7 to 14 days
Acute Uncomplicated Cystitis | 250 mg | every 12 hours | 3 days
Acute Sinusitis | 500 mg | every 12 hours | 10 days

- Adults with creatinine clearance 30–50 mL/min 250–500 mg q 12 h (2.3)
- Adults with creatinine clearance 5–29 mL/min 250–500 mg q 18 h (2.3)
- Patients on hemodialysis or peritoneal dialysis 250–500 mg q 24 h (after dialysis) (2.3)

Pediatric Oral Dosage Guidelines
Infection | Dose | Frequency | Duration
Complicated UTI and Pyelonephritis; (1 to 17 years of age) | 10–20 mg/kg; (maximum 750 mg per dose) | Every 12 hours | 10–21 days
Inhalational Anthrax; (Post-Exposure) | 15 mg/kg; (maximum 500 mg per dose) | Every 12 hours | 60 days
Plague | 15 mg/kg (maximum 500 mg per dose) | Every 8 to 12 hours | 14 days

3 DOSAGE FORMS AND STRENGTHS

- Tablets: 250 mg, functionally scored and 500 mg, functionally scored (3)
- Oral Suspension: 5% (250 mg/5 mL), 10% (500 mg/5 mL) (3)

4 CONTRAINDICATIONS

- Known hypersensitivity to CIPRO or other quinolones (4.1, 5.6, 5.7)
- Concomitant administration with tizanidine (4.2)

5 WARNINGS AND PRECAUTIONS

- Hypersensitivity and other serious reactions: Serious and sometimes fatal reactions (for example, anaphylactic reactions) may occur after the first or subsequent doses of CIPRO. Discontinue CIPRO at the first sign of skin rash, jaundice or any sign of hypersensitivity. (4.1, 5.6, 5.7)
- Hepatotoxicity: Discontinue immediately if signs and symptoms of hepatitis occur. (5.8)
- Clostridioides difficile-associated diarrhea: Evaluate if colitis occurs. (5.11)
- QT Prolongation: Prolongation of the QT interval and isolated cases of torsade de pointes have been reported. Avoid use in patients with known prolongation, those with hypokalemia, and with other drugs that prolong the QT interval. (5.12, 7, 8.5)

6 ADVERSE REACTIONS

The most common adverse reactions ≥1% were nausea, diarrhea, liver function tests abnormal, vomiting, and rash. (6)

To report SUSPECTED ADVERSE REACTIONS, contact Bayer HealthCare Pharmaceuticals Inc. at 1-888-842-2937 or FDA at 1-800-FDA-1088 or www.fda.gov/medwatch.

7 DRUG INTERACTIONS

Interacting Drug | Interaction
Theophylline | Serious and fatal reactions. Avoid concomitant use. Monitor serum level (7)
Warfarin | Anticoagulant effect enhanced. Monitor prothrombin time, INR, and bleeding (7)
Antidiabetic agents | Hypoglycemia including fatal outcomes have been reported. Monitor blood glucose (7)
Phenytoin | Monitor phenytoin level (7)
Methotrexate | Monitor for methotrexate toxicity (7)
Cyclosporine | May increase serum creatinine. Monitor serum creatinine (7)
Multivalent cation-containing products including antacids, metal cations or didanosine | Decreased CIPRO absorption. Take CIPRO 2 hours before or 6 hours after administration of multivalent cation containing drugs (7)

8 USE IN SPECIFIC POPULATIONS

Lactation: Breastfeeding is not recommended during treatment, but a lactating
  woman may pump and discard breastmilk during treatment and an additional 2 days after the last dose. In patients treated for inhalational anthrax (post exposure), consider the risks and benefits of continuing breastfeeding. (8.2)
See full prescribing information for use in pediatric and geriatric patients (8.4, 8.5)

FULL PRESCRIBING INFORMATION

WARNING: SERIOUS ADVERSE REACTIONS INCLUDING TENDINITIS, TENDON RUPTURE, PERIPHERAL NEUROPATHY, CENTRAL NERVOUS SYSTEM EFFECTS AND EXACERBATION OF MYASTHENIA GRAVIS

- Fluoroquinolones, including CIPRO®, have been associated with disabling and potentially irreversible serious adverse reactions that have occurred together [see Warnings and Precautions (5.1)], including:
  - Tendinitis and tendon rupture [see Warnings and Precautions (5.2)].
  - Peripheral neuropathy [see Warnings and Precautions (5.3)].
  - Central nervous system effects [see Warnings and Precautions (5.4)].
Discontinue CIPRO immediately and avoid the use of fluoroquinolones, including CIPRO, in patients who experience any of these serious adverse reactions [see Warnings and Precautions (5.1)].
- Fluoroquinolones, including CIPRO, may exacerbate muscle weakness in patients with myasthenia gravis. Avoid CIPRO in patients with known history of myasthenia gravis. [see Warnings and Precautions (5.5)].
- Because fluoroquinolones, including CIPRO, have been associated with serious adverse reactions [see Warnings and Precautions (5.1-5.16)], reserve CIPRO for use in patients who have no alternative treatment options for the following indications:
  - Acute exacerbation of chronic bronchitis [see Indications and Usage (1.10)].
  - Acute uncomplicated cystitis [see Indications and Usage (1.11)].
  - Acute sinusitis [see Indications and Usage (1.12)].

1 INDICATIONS AND USAGE

1.1 Skin and Skin Structure Infections

CIPRO is indicated in adult patients for treatment of skin and skin structure infections caused by Escherichia coli, Klebsiella pneumoniae, Enterobacter cloacae, Proteus mirabilis, Proteus vulgaris, Providencia stuartii, Morganella morganii, Citrobacter freundii, Pseudomonas aeruginosa, methicillin-susceptible Staphylococcus aureus, methicillin-susceptible Staphylococcus epidermidis, or Streptococcus pyogenes.

1.2 Bone and Joint Infections

CIPRO is indicated in adult patients for treatment of bone and joint infections caused by Enterobacter cloacae, Serratia marcescens, or Pseudomonas aeruginosa.

1.3 Complicated Intra-Abdominal Infections

CIPRO is indicated in adult patients for treatment of complicated intra-abdominal infections (used in combination with metronidazole) caused by Escherichia coli, Pseudomonas aeruginosa, Proteus mirabilis, Klebsiella pneumoniae, or Bacteroides fragilis.

1.4 Infectious Diarrhea

CIPRO is indicated in adult patients for treatment of infectious diarrhea caused by Escherichia coli (enterotoxigenic isolates), Campylobacter jejuni, Shigella boydii †, Shigella dysenteriae, Shigella flexneri or Shigella sonnei† when antibacterial therapy is indicated.

†Although treatment of infections due to this organism in this organ system demonstrated a clinically significant outcome, efficacy was studied in fewer than 10 patients.

1.5 Typhoid Fever (Enteric Fever)

CIPRO is indicated in adult patients for treatment of typhoid fever (enteric fever) caused by Salmonella typhi. The efficacy of ciprofloxacin in the eradication of the chronic typhoid carrier state has not been demonstrated.

1.6 Uncomplicated Cervical and Urethral Gonorrhea

CIPRO is indicated in adult patients for treatment of uncomplicated cervical and urethral gonorrhea due to Neisseria gonorrhoeae [see Warnings and Precautions (5.17)].

1.7 Inhalational Anthrax (Post-Exposure)

CIPRO is indicated in adults and pediatric patients from birth to 17 years of age for inhalational anthrax (post-exposure) to reduce the incidence or progression of disease following exposure to aerosolized Bacillus anthracis.

Ciprofloxacin serum concentrations achieved in humans served as a surrogate endpoint reasonably likely to predict clinical benefit and provided the initial basis for approval of this indication.^1 Supportive clinical information for ciprofloxacin for anthrax post-exposure prophylaxis was obtained during the anthrax bioterror attacks of October 2001 [see Clinical Studies (14.2)].

1.8 Plague

CIPRO is indicated for treatment of plague, including pneumonic and septicemic plague, due to Yersinia pestis (Y. pestis) and prophylaxis for plague in adults and pediatric patients from birth to 17 years of age. Efficacy studies of ciprofloxacin could not be conducted in humans with plague for feasibility reasons. Therefore this indication is based on an efficacy study conducted in animals only [see Clinical Studies (14.3)].

1.9 Chronic Bacterial Prostatitis

CIPRO is indicated in adult patients for treatment of chronic bacterial prostatitis caused by Escherichia coli or Proteus mirabilis.

1.10 Lower Respiratory Tract Infections

CIPRO is indicated in adult patients for treatment of lower respiratory tract infections caused by Escherichia coli, Klebsiella pneumoniae, Enterobacter cloacae, Proteus mirabilis, Pseudomonas aeruginosa, Haemophilus influenzae, Haemophilus parainfluenzae, or Streptococcus pneumoniae.

CIPRO is not a drug of first choice in the treatment of presumed or confirmed pneumonia secondary to Streptococcus pneumoniae.

CIPRO is indicated for the treatment of acute exacerbations of chronic bronchitis (AECB) caused by Moraxella catarrhalis.

Because fluoroquinolones, including CIPRO, have been associated with serious adverse reactions [see Warnings and Precautions (5.1–5.16)] and for some patients AECB is self-limiting, reserve CIPRO for treatment of AECB in patients who have no alternative treatment options.

1.11 Urinary Tract Infections

Urinary Tract Infections in Adults

CIPRO is indicated in adult patients for treatment of urinary tract infections caused by Escherichia coli, Klebsiella pneumoniae, Enterobacter cloacae, Serratia marcescens, Proteus mirabilis, Providencia rettgeri, Morganella morganii, Citrobacter koseri, Citrobacter freundii, Pseudomonas aeruginosa, methicillin-susceptible Staphylococcus epidermidis, Staphylococcus saprophyticus, or Enterococcus faecalis.

Acute Uncomplicated Cystitis

CIPRO is indicated in adult female patients for treatment of acute uncomplicated cystitis caused by Escherichia coli or Staphylococcus saprophyticus.

Because fluoroquinolones, including CIPRO, have been associated with serious adverse reactions [see Warnings and Precautions (5.1-5.16)] and for some patients acute uncomplicated cystitis is self-limiting, reserve CIPRO for treatment of acute uncomplicated cystitis in patients who have no alternative treatment options.

Complicated Urinary Tract Infection and Pyelonephritis in Pediatric Patients

CIPRO is indicated in pediatric patients aged one to 17 years of age for treatment of complicated urinary tract infections (cUTI) and pyelonephritis due to Escherichia coli [see Use in Specific Populations (8.4)].

Although effective in clinical trials, CIPRO is not a drug of first choice in the pediatric population due to an increased incidence of adverse reactions compared to controls, including reactions related to joints and/or surrounding tissues. CIPRO, like other fluoroquinolones, is associated with arthropathy and histopathological changes in weight-bearing joints of juvenile animals [see Warnings and Precautions (5.13), Adverse Reactions (6.1), Use in Specific Populations (8.4) and Nonclinical Toxicology (13.2)].

1.12 Acute Sinusitis

CIPRO is indicated in adult patients for treatment of acute sinusitis caused by Haemophilus influenzae, Streptococcus pneumoniae, or Moraxella catarrhalis.

Because fluoroquinolones, including CIPRO, have been associated with serious adverse reactions [see Warnings and Precautions (5.1-5.16)] and for some patients acute sinusitis is self-limiting, reserve CIPRO for treatment of acute sinusitis in patients who have no alternative treatment options.

1.13 Usage

To reduce the development of drug-resistant bacteria and maintain the effectiveness of CIPRO and other antibacterial drugs, CIPRO should be used only to treat or prevent infections that are proven or strongly suspected to be caused by susceptible bacteria. When culture and susceptibility information are available, they should be considered in selecting or modifying antibacterial therapy. In the absence of such data, local epidemiology and susceptibility patterns may contribute to the empiric selection of therapy.

If anaerobic organisms are suspected of contributing to the infection, appropriate therapy should be administered. Appropriate culture and susceptibility tests should be performed before treatment in order to isolate and identify organisms causing infection and to determine their susceptibility to ciprofloxacin. Therapy with CIPRO may be initiated before results of these tests are known; once results become available appropriate therapy should be continued.

As with other drugs, some isolates of Pseudomonas aeruginosa may develop resistance fairly rapidly during treatment with ciprofloxacin. Culture and susceptibility testing performed periodically during therapy will provide information not only on the therapeutic effect of the antimicrobial agent but also on the possible emergence of bacterial resistance.

2 DOSAGE AND ADMINISTRATION

CIPRO Tablets and Oral Suspension should be administered orally as described in the appropriate Dosage Guidelines tables.

2.1 Dosage in Adults

The determination of dosage and duration for any particular patient must take into consideration the severity and nature of the infection, the susceptibility of the causative microorganism, the integrity of the patient’s host-defense mechanisms, and the status of renal and hepatic function. CIPRO Tablets or CIPRO for Oral Suspension may be administered to adult patients when clinically indicated at the discretion of the physician. Administer CIPRO for Oral Suspension using the co-packaged graduated spoon [see Dosage and Administration (2.7)].

Table 1: Adult Dosage Guidelines
Infection | Dose | Frequency | Usual Durations [Generally ciprofloxacin should be continued for at least 2 days after the signs and symptoms of infection have disappeared, except for inhalational anthrax (post-exposure).]
Skin and Skin Structure | 500–750 mg | every 12 hours | 7 to 14 days
Bone and Joint | 500–750 mg | every 12 hours | 4 to 8 weeks
Complicated Intra–Abdominal [Used in conjunction with metronidazole.] | 500 mg | every 12 hours | 7 to 14 days
Infectious Diarrhea | 500 mg | every 12 hours | 5 to 7 days
Typhoid Fever | 500 mg | every 12 hours | 10 days
Uncomplicated Urethral and Cervical Gonococcal Infections | 250 mg | single dose | single dose
Inhalational anthrax (post-exposure) [Begin drug administration as soon as possible after suspected or confirmed exposure.] | 500 mg | every 12 hours | 60 days
Plague | 500–750 mg | every 12 hours | 14 days
Chronic Bacterial Prostatitis | 500 mg | every 12 hours | 28 days
Lower Respiratory Tract Infections | 500–750 mg | every 12 hours | 7 to 14 days
Urinary Tract Infections | 250–500 mg | every 12 hours | 7 to 14 days
Acute Uncomplicated Cystitis | 250 mg | every 12 hours | 3 days
Acute Sinusitis | 500 mg | every 12 hours | 10 days

Conversion of IV to Oral Dosing in Adults

Patients whose therapy is started with CIPRO IV may be switched to CIPRO Tablets or Oral Suspension when clinically indicated at the discretion of the physician (Table 2) [see Clinical Pharmacology (12.3)].

Table 2: Equivalent AUC Dosing Regimens
CIPRO Oral Dosage | Equivalent CIPRO IV Dosage
250 mg Tablet every 12 hours | 200 mg intravenous every 12 hours
500 mg Tablet every 12 hours | 400 mg intravenous every 12 hours
750 mg Tablet every 12 hours | 400 mg intravenous every 8 hours

2.2 Dosage in Pediatric Patients

Dosing and initial route of therapy (that is, IV or oral) for cUTI or pyelonephritis should be determined by the severity of the infection. CIPRO should be administered as described in Table 3. Administer CIPRO for Oral Suspension using the co-packaged graduated spoon [see Dosage and Administration (2.7)].

Table 3: Pediatric Dosage Guidelines
Infection | Dose | Frequency | Total Duration
Complicated Urinary Tract or Pyelonephritis; (patients from 1 to 17 years of age) | 10 mg/kg to 20 mg/kg; (maximum 750 mg per dose; not to be exceeded even in patients weighing more than 51 kg) | Every 12 hours | 10–21 days^1
Inhalational Anthrax (Post-Exposure)^2 | 15 mg/kg; (maximum 500 mg per dose) | Every 12 hours | 60 days
Plague^2,3 | 15 mg/kg; (maximum 500 mg per dose) | Every 8 to 12 hours | 14 days

^1 The total duration of therapy for cUTI and pyelonephritis in the clinical trial was determined by the physician. The mean duration of treatment was 11 days (range 10 to 21 days).

^2Begin drug administration as soon as possible after suspected or confirmed exposure.

^3Begin drug administration as soon as possible after suspected or confirmed exposure to Y. pestis.

2.3 Dosage Modifications in Patients with Renal Impairment

Ciprofloxacin is eliminated primarily by renal excretion; however, the drug is also metabolized and partially cleared through the biliary system of the liver and through the intestine. These alternative pathways of drug elimination appear to compensate for the reduced renal excretion in patients with renal impairment. Nonetheless, some modification of dosage is recommended, particularly for patients with severe renal dysfunction. Dosage guidelines for use in patients with renal impairment are shown in Table 4.

Table 4: Recommended Starting and Maintenance Doses for Adult Patients with Impaired Renal Function
Creatinine Clearance (mL/min) | Dose
> 50 | See Usual Dosage.
30–50 | 250–500 mg every 12 hours
5–29 | 250–500 mg every 18 hours
Patients on hemodialysis or Peritoneal dialysis | 250–500 mg every 24 hours (after dialysis)

When only the serum creatinine concentration is known, the following formulas may be used to estimate creatinine clearance:

Men - Creatinine clearance (mL/min) = Weight (kg) x (140–age)

72 x serum creatinine (mg/dL)

Women - 0.85 x the value calculated for men.

The serum creatinine should represent a steady state of renal function.

In patients with severe infections and severe renal impairment, a unit dose of 750 mg may be administered at the intervals noted above. Patients should be carefully monitored.

Pediatric patients with moderate to severe renal insufficiency were excluded from the clinical trial of cUTI and pyelonephritis. No information is available on dosing adjustments necessary for pediatric patients with moderate to severe renal insufficiency (that is, creatinine clearance of < 50 mL/min/1.73m^2).

2.4 Important Administration Instructions

With Multivalent Cations

Administer CIPRO at least 2 hours before or 6 hours after magnesium/aluminum antacids; polymeric phosphate binders (for example, sevelamer, lanthanum carbonate) or sucralfate; Videx® (didanosine) chewable/buffered tablets or pediatric powder for oral solution; other highly buffered drugs; or other products containing calcium, iron or zinc.

With Dairy Products

Concomitant administration of CIPRO with dairy products (like milk or yogurt) or calcium-fortified juices alone should be avoided since decreased absorption is possible; however, CIPRO may be taken with a meal that contains these products.

Hydration of Patients Receiving CIPRO

Assure adequate hydration of patients receiving CIPRO to prevent the formation of highly concentrated urine. Crystalluria has been reported with quinolones.

Instruct the patient of the appropriate CIPRO administration [see Patient Counseling Information (17)].

Missed Doses

If a dose is missed, it should be taken anytime but not later than 6 hours prior to the next scheduled dose. If less than 6 hours remain before the next dose, the missed dose should not be taken and treatment should be continued as prescribed with the next scheduled dose. Double doses should not be taken to compensate for a missed dose.

Splitting CIPRO Tablets

CIPRO Tablets, 250 mg and 500 mg are functionally scored tablets which can be split into one-half at the scored line to provide a 125 mg and 250 mg strength, respectively.

2.5 Directions for Reconstitution of the CIPRO Microcapsules for Oral Suspension

CIPRO Oral Suspension is supplied in 5% (5 g ciprofloxacin in 100 mL) and 10% (10 g ciprofloxacin in 100 mL) strengths. CIPRO oral suspension is composed of two components (microcapsules and diluent) that must be combined prior to dispensing.

Table 5: Appropriate Dosing Volumes of the Reconstituted Oral Suspensions
Dose | 5%; (250 mg/5 mL) | 10%; (500 mg/5 mL)
250 mg | 5 mL | 2.5 mL
500 mg | 10 mL | 5 mL
750 mg | 15 mL | 7.5 mL

Preparation of the suspension:

Step1 | The small bottle contains the microcapsules, the large bottle contains the diluent. | Step 2 | Open both bottles. Child-proof cap: Press down according to instructions on the cap while turning to the left.
Step 3 | Pour the microcapsules completely into the larger bottle of diluent. Do not add water to the suspension. | Step 4 | Remove the top layer of the diluent bottle label (to reveal the CIPRO Oral Suspension label). Close the large bottle completely according to the directions on the cap and shake vigorously for about 15 seconds. The suspension is ready for use.

Step 5: Write the expiration date of the re-constituted oral suspension on the bottle label.

Reconstituted product may be stored below 30°C (86°F) for 14 days. Protect from freezing.

No additions should be made to the mixed final ciprofloxacin suspension. CIPRO Oral Suspension should not be administered through feeding or NG (nasogastric) tubes due to its physical characteristics.

2.6 Administration Instructions for CIPRO for Oral Suspension After Reconstitution

- Shake CIPRO Oral Suspension vigorously each time before use for approximately 15 seconds.
- Administer CIPRO Oral Suspension using the co-packaged graduated teaspoon provided for the patient (see Figure 1)

Figure 1: Co-packaged 5 mL graduated teaspoon

The Co-packaged graduated teaspoon (5mL) is provided, with markings for 1/2 (2.5 mL) and 1/1 (5 mL)

- After use, clean the graduated teaspoon under running water with dish detergent and dry thoroughly.
- Do Not chew the microcapsules in the CIPRO Oral Suspension, instead swallow them whole.
- Water may be taken afterwards.
- Reclose the bottle properly after each use according to instructions on the cap.
- After treatment has been completed, CIPRO Oral Suspension should not be reused.

2.7 Dosing of CIPRO for Oral Suspension using the Co-Packaged Spoon in Adults and Pediatric Patients

Table 6: 5% Cipro for Oral Suspension: 250 mg ciprofloxacin per 5 mL after reconstitution

Infection | Body weight (kg) | Dose by Measuring Spoonful(s) using Co-Packed Spoon* (teaspoonful (s) (volume (mL)) | Dose Strength; (mg)
Complicated Urinary Tract or Pyelonephritis (patients from 1 to 17 years of age)^1; and Plague^2 | 9 kg to 12 kg | ½ teaspoonful (2.5 mL) | 125 mg
 | 13 kg to 18 kg | 1 teaspoonful (5 mL) | 250 mg
 | 19 kg to 24 kg | 1 to 1 ½ teaspoonful(s) (5 mL to 7.5 mL) | 250 mg to 375 mg
 | 25 kg to 31 kg | 1 ½ to 2 teaspoonfuls (7.5 mL to 10 mL) | 375 mg to 500 mg
 | 32 kg to 37 kg | 1 ½ to 2 ½ teaspoonfuls (7.5 mL to 12.5 mL) | 375 mg to 625 mg
 | 38 kg or more | 2 to 3 teaspoonfuls (10 mL to 15 mL) | 500 mg to 750 mg
Inhalational Anthrax (Post-Exposure)^3 | 9 kg to 12 kg | ½ teaspoonful (2.5 mL) | 125 mg
 | 13 kg to 18 kg | 1 teaspoonful (5 mL) | 250 mg
 | 19 kg to 24 kg | 1 to 1 ½ teaspoonful(s) (5 mL to 7.5 mL) | 250 mg to 375 mg
 | 25 kg or more | 2 teaspoonfuls (10 mL) | 500 mg

* A graduated teaspoon (5mL) with markings 1/2 (2.5) mL and 1/1 (5 mL) is provided for the patient.

^1Administer every 12 hours for 10-21 days [see Dosage and Administration (2.2)]

^2Administer every 8-12 hours for 10-21 days for Pediatric patients [see Dosage and Administration (2.2)]; for adults administer every 12 hours for 14 days [see Dosage and Administration (2.1)]

^3Administer every 12 hours for 60 days [see Dosage and Administration (2.1 and 2.2)]

Table 7: 10% Oral Suspension: 500 mg ciprofloxacin per 5 mL after reconstitution (not appropriate for children weighing less than 13 kg)
Infection | Body weight (kg) | Dose by Measuring Spoonful(s) using Co-Packed Spoon* (teaspoonful (s) (volume (mL)) | Dose Strength; (mg)
Complicated Urinary Tract or Pyelonephritis (patients from 1 to 17 years of age)^1; and Plague^2 | 13 kg to 24 kg | ½ teaspoonful (2.5 mL) | 250 mg
 | 25 kg | ½ to 1 teaspoonful (2.5 mL to 5 mL) | 250 mg to 500 mg
 | 26 kg to 37 kg | 1 teaspoonful (5 mL) | 500 mg
 | 38 kg or more | 1 to 1½ teaspoonful(s) (5 mL to 7.5 mL) | 500 mg to maximum dose of 750 mg
Inhalational Anthrax (Post-Exposure)^3 | 13 kg to 24 kg | ½ teaspoonful (2.5 mL) | 250 mg
 | 25 kg or more | 1 teaspoonful (5 mL) | 500 mg

* A graduated teaspoon (5mL) with markings 1/2 (2.5) mL and 1/1 (5 mL) is provided for the patient.

^1Administer every 12 hours for 10-21 days [see Dosage and Administration (2.2)]

^2Administer every 8-12 hours for 10-21 days for Pediatric patients [see Dosage and Administration (2.2)]; for adults administer every 12 hours for 14 days [see Dosage and Administration (2.1)]

^3Administer every 12 hours for 60 days [see Dosage and Administration (2.1 and 2.2)]

3 DOSAGE FORMS AND STRENGTHS

3.1 Tablets

- 250 mg, slightly yellowish, film-coated, round, functionally scored, imprinted with “BAYER” on one side and “CIP 250” on the other
- 500 mg, slightly yellowish, film-coated, capsule shaped, functionally scored, imprinted with “BAYER” on one side and “CIP 500” on the other

3.2 Oral Suspension

- 5% Oral Suspension: 250 mg ciprofloxacin per 5 mL after reconstitution
- 10% Oral Suspension: 500 mg ciprofloxacin per 5 mL after reconstitution

4 CONTRAINDICATIONS

4.1 Hypersensitivity

CIPRO is contraindicated in persons with a history of hypersensitivity to ciprofloxacin, any member of the quinolone class of antibacterials, or any of the product components [see Warnings and Precautions (5.7)].

4.2 Tizanidine

Concomitant administration with tizanidine is contraindicated [see Drug Interactions (7)].

5 WARNINGS AND PRECAUTIONS

5.1 Disabling and Potentially Irreversible Serious Adverse Reactions Including Tendinitis and Tendon Rupture, Peripheral Neuropathy, and Central Nervous System Effects

Fluoroquinolones, including CIPRO, have been associated with disabling and potentially irreversible serious adverse reactions from different body systems that can occur together in the same patient. Commonly seen adverse reactions include tendinitis, tendon rupture, arthralgia, myalgia, peripheral neuropathy, and central nervous system effects (hallucinations, anxiety, depression, insomnia, severe headaches, and confusion). These reactions can occur within hours to weeks after starting CIPRO. Patients of any age or without pre-existing risk factors have experienced these adverse reactions [see Warnings and Precautions (5.2, 5.3, 5.4)].

Discontinue CIPRO immediately at the first signs or symptoms of any serious adverse reaction. In addition, avoid the use of fluoroquinolones, including CIPRO, in patients who have experienced any of these serious adverse reactions associated with fluoroquinolones.

5.2 Tendinitis and Tendon Rupture

Fluoroquinolones, including CIPRO, have been associated with an increased risk of tendinitis and tendon rupture in all ages [see Warnings and Precautions (5.1) and Adverse Reactions (6.2)]. This adverse reaction most frequently involves the Achilles tendon, and has also been reported with the rotator cuff (the shoulder), the hand, the biceps, the thumb, and other tendons. Tendinitis or tendon rupture can occur, within hours or days of starting CIPRO, or as long as several months after completion of fluoroquinolone therapy. Tendinitis and tendon rupture can occur bilaterally.

The risk of developing fluoroquinolone-associated tendinitis and tendon rupture is increased in patients over 60 years of age, in patients taking corticosteroid drugs, and in patients with kidney, heart or lung transplants. Other factors that may independently increase the risk of tendon rupture include strenuous physical activity, renal failure, and previous tendon disorders such as rheumatoid arthritis. Tendinitis and tendon rupture have also occurred in patients taking fluoroquinolones who do not have the above risk factors. Discontinue CIPRO immediately if the patient experiences pain, swelling, inflammation or rupture of a tendon. Avoid fluoroquinolones, including CIPRO, in patients who have a history of tendon disorders or have experienced tendinitis or tendon rupture [see Adverse Reactions (6.2)].

5.3 Peripheral Neuropathy

Fluoroquinolones, including CIPRO, have been associated with an increased risk of peripheral neuropathy. Cases of sensory or sensorimotor axonal polyneuropathy affecting small and/or large axons resulting in paresthesias, hypoesthesias, dysesthesias and weakness have been reported in patients receiving fluoroquinolones, including CIPRO. Symptoms may occur soon after initiation of CIPRO and may be irreversible in some patients [see Warnings and Precautions (5.1) and Adverse Reactions (6.1, 6.2)].

Discontinue CIPRO immediately if the patient experiences symptoms of peripheral neuropathy including pain, burning, tingling, numbness, and/or weakness, or other alterations in sensations including light touch, pain, temperature, position sense and vibratory sensation, and/or motor strength in order to minimize the development of an irreversible condition. Avoid fluoroquinolones, including CIPRO, in patients who have previously experienced peripheral neuropathy [see Adverse Reactions (6.1, 6.2)].

5.4 Central Nervous System Effects

Psychiatric Adverse Reactions

Fluoroquinolones, including CIPRO, have been associated with an increased risk of psychiatric adverse reactions, including: toxic psychosis, psychotic reactions progressing to suicidal ideations/thoughts, hallucinations, or paranoia; depression, or self-injurious behavior such as attempted or completed suicide; anxiety, agitation, or nervousness; confusion, delirium, disorientation, or disturbances in attention; insomnia or nightmares; memory impairment. These reactions may occur following the first dose. Advise patients receiving CIPRO to inform their healthcare provider immediately if these reactions occur, discontinue the drug, and institute appropriate care.

Central Nervous System Adverse Reactions

Fluoroquinolones, including CIPRO, have been associated with an increased risk of seizures (convulsions), increased intracranial pressure (pscudotumor cerebri), dizziness, and tremors. CIPRO, like other fluoroquinolones, is known to trigger seizures or lower the seizure threshold. Cases of status epilepticus have been reported. As with all fluoroquinolones, use CIPRO with caution in epileptic patients and patients with known or suspected CNS disorders that may predispose to seizures or lower the seizure threshold (for example, severe cerebral arteriosclerosis, previous history of convulsion, reduced cerebral blood flow, altered brain structure, or stroke), or in the presence of other risk factors that may predispose to seizures or lower the seizure threshold (for example, certain drug therapy, renal dysfunction). If seizures occur, discontinue CIPRO and institute appropriate care [see Adverse Reactions (6.1) and Drug Interactions (7)].

5.5 Exacerbation of Myasthenia Gravis

Fluoroquinolones, including CIPRO, have neuromuscular blocking activity and may exacerbate muscle weakness in patients with myasthenia gravis. Postmarketing serious adverse reactions, including deaths and requirement for ventilatory support, have been associated with fluoroquinolone use in patients with myasthenia gravis. Avoid CIPRO in patients with known history of myasthenia gravis [see Adverse Reactions (6.2)].

5.6 Other Serious and Sometimes Fatal Adverse Reactions

Other serious and sometimes fatal adverse reactions, some due to hypersensitivity, and some due to uncertain etiology, have been reported in patients receiving therapy with quinolones, including CIPRO. These events may be severe and generally occur following the administration of multiple doses. Clinical manifestations may include one or more of the following:

- Fever, rash, or severe dermatologic reactions (for example, toxic epidermal necrolysis, Stevens-Johnson syndrome);
- Vasculitis; arthralgia; myalgia; serum sickness;
- Allergic pneumonitis;
- Interstitial nephritis; acute renal insufficiency or failure;
- Hepatitis; jaundice; acute hepatic necrosis or failure;
- Anemia, including hemolytic and aplastic; thrombocytopenia, including thrombotic thrombocytopenic purpura; leukopenia; agranulocytosis; pancytopenia; and/or other hematologic abnormalities.

Discontinue CIPRO immediately at the first appearance of a skin rash, jaundice, or any other sign of hypersensitivity and supportive measures instituted [see Adverse Reactions (6.1, 6.2)].

5.7 Hypersensitivity Reactions

Serious and occasionally fatal hypersensitivity (anaphylactic) reactions, some following the first dose, have been reported in patients receiving fluoroquinolone therapy, including CIPRO. Some reactions were accompanied by cardiovascular collapse, acute myocardial ischemia with or without myocardial infarction, loss of consciousness, tingling, pharyngeal or facial edema, dyspnea, urticaria, and itching. Only a few patients had a history of hypersensitivity reactions. Serious anaphylactic reactions require immediate emergency treatment with epinephrine and other resuscitation measures, including oxygen, intravenous fluids, intravenous antihistamines, corticosteroids, pressor amines, and airway management, including intubation, as indicated [see Adverse Reactions (6.1, 6.2)].

5.8 Hepatotoxicity

Cases of severe hepatotoxicity, including hepatic necrosis, life-threatening hepatic failure, and fatal events, have been reported with CIPRO. Acute liver injury is rapid in onset (range 1–39 days), and is often associated with hypersensitivity. The pattern of injury can be hepatocellular, cholestatic, or mixed. Most patients with fatal outcomes were older than 55 years old. In the event of any signs and symptoms of hepatitis (such as anorexia, jaundice, dark urine, pruritus, or tender abdomen), discontinue treatment immediately.

There can be a temporary increase in transaminases, alkaline phosphatase, or cholestatic jaundice, especially in patients with previous liver damage, who are treated with CIPRO [see Adverse Reactions (6.2, 6.3)].

5.9 Risk of Aortic Aneurysm and Dissection

Epidemiologic studies report an increased rate of aortic aneurysm and dissection within two months following use of fluoroquinolones, particularly in elderly patients. The cause for the increased risk has not been identified. In patients with a known aortic aneurysm or patients who are at greater risk for aortic aneurysms, reserve CIPRO for use only when there are no alternative antibacterial treatments available.

5.10 Serious Adverse Reactions with Concomitant Theophylline

Serious and fatal reactions have been reported in patients receiving concurrent administration of CIPRO and theophylline. These reactions have included cardiac arrest, seizure, status epilepticus, and respiratory failure. Instances of nausea, vomiting, tremor, irritability, or palpitation have also occurred.

Although similar serious adverse reactions have been reported in patients receiving theophylline alone, the possibility that these reactions may be potentiated by CIPRO cannot be eliminated. If concomitant use cannot be avoided, monitor serum levels of theophylline and adjust dosage as appropriate [see Drug Interactions (7)].

5.11 Clostridioides difficile-Associated Diarrhea

Clostridioides difficile (C. difficile)-associated diarrhea (CDAD) has been reported with use of nearly all antibacterial agents, including CIPRO, and may range in severity from mild diarrhea to fatal colitis. Treatment with antibacterial agents alters the normal flora of the colon leading to overgrowth of C. difficile.

C. difficile produces toxins A and B which contribute to the development of CDAD. Hypertoxin producing isolates of C. difficile cause increased morbidity and mortality, as these infections can be refractory to antimicrobial therapy and may require colectomy. CDAD must be considered in all patients who present with diarrhea following antibacterial use. Careful medical history is necessary since CDAD has been reported to occur over two months after the administration of antibacterial agents.

If CDAD is suspected or confirmed, ongoing antibacterial use not directed against C. difficile may need to be discontinued. Appropriate fluid and electrolyte management, protein supplementation, antibacterial treatment of C. difficile, and institute surgical evaluation as clinically indicated [see Adverse Reactions (6.1)].

5.12 Prolongation of the QT Interval

Some fluoroquinolones, including CIPRO, have been associated with prolongation of the QT interval on the electrocardiogram and cases of arrhythmia. Cases of torsade de pointes have been reported during postmarketing surveillance in patients receiving fluoroquinolones, including CIPRO.

Avoid CIPRO in patients with known prolongation of the QT interval, risk factors for QT prolongation or torsade de pointes (for example, congenital long QT syndrome, uncorrected electrolyte imbalance, such as hypokalemia or hypomagnesemia and cardiac disease, such as heart failure, myocardial infarction, or bradycardia), and patients receiving Class IA antiarrhythmic agents (quinidine, procainamide), or Class III antiarrhythmic agents (amiodarone, sotalol), tricyclic antidepressants, macrolides, and antipsychotics. Elderly patients may also be more susceptible to drug-associated effects on the QT interval [see Adverse Reactions (6.2), Use in Specific Populations (8.5)].

5.13 Musculoskeletal Disorders in Pediatric Patients and Arthropathic Effects in Animals

CIPRO is indicated in pediatric patients (less than 18 years of age) only for cUTI, prevention of inhalational anthrax (post exposure), and plague [see Indications and Usage (1.7, 1.8, 1.11)]. An increased incidence of adverse reactions compared to controls, including reactions related to joints and/or surrounding tissues, has been observed [see Adverse Reactions (6.1)].

In pre-clinical studies, oral administration of CIPRO caused lameness in immature dogs. Histopathological examination of the weight-bearing joints of these dogs revealed permanent lesions of the cartilage. Related quinolone-class drugs also produce erosions of cartilage of weight-bearing joints and other signs of arthropathy in immature animals of various species [see Use in Specific Populations (8.4) and Nonclinical Toxicology (13.2)].

5.14 Photosensitivity/Phototoxicity

Moderate to severe photosensitivity/phototoxicity reactions, the latter of which may manifest as exaggerated sunburn reactions (for example, burning, erythema, exudation, vesicles, blistering, edema) involving areas exposed to light (typically the face, “V” area of the neck, extensor surfaces of the forearms, dorsa of the hands), can be associated with the use of quinolones including CIPRO after sun or UV light exposure. Therefore, avoid excessive exposure to these sources of light. Discontinue CIPRO if phototoxicity occurs [see Adverse Reactions (6.1)].

5.15 Development of Drug Resistant Bacteria

Prescribing CIPRO Tablets and CIPRO Oral Suspension in the absence of a proven or strongly suspected bacterial infection or a prophylactic indication is unlikely to provide benefit to the patient and increases the risk of the development of drug-resistant bacteria.

5.16 Potential Risks with Concomitant Use of Drugs Metabolized by Cytochrome P450 1A2 Enzymes

CIPRO is an inhibitor of the hepatic CYP1A2 enzyme pathway. Co-administration of CIPRO and other drugs primarily metabolized by CYP1A2 (for example, theophylline, methylxanthines, caffeine, tizanidine, ropinirole, clozapine, olanzapine and zolpidem), results in increased plasma concentrations of the co-administered drug and could lead to clinically significant pharmacodynamic adverse reactions of the co-administered drug [see Drug Interactions (7) and Clinical Pharmacology (12.3)].

5.17 Interference with Timely Diagnosis of Syphilis

CIPRO has not been shown to be effective in the treatment of syphilis. Antimicrobial agents used in high dose for short periods of time to treat gonorrhea may mask or delay the symptoms of incubating syphilis. Perform a serologic test for syphilis in all patients with gonorrhea at the time of diagnosis. Perform follow-up serologic test for syphilis three months after CIPRO treatment.

5.18 Crystalluria

Crystals of ciprofloxacin have been observed rarely in the urine of human subjects but more frequently in the urine of laboratory animals, which is usually alkaline [see Nonclinical Toxicology (13.2)]. Crystalluria related to CIPRO has been reported only rarely in humans because human urine is usually acidic. Avoid alkalinity of the urine in patients receiving CIPRO. Hydrate patients well to prevent the formation of highly concentrated urine [see Dosage and Administration (2.4)].

5.19 Blood Glucose Disturbances

Fluoroquinolones, including CIPRO, have been associated with disturbances of blood glucose, including symptomatic hyperglycemia and hypoglycemia, usually in diabetic patients receiving concomitant treatment with an oral hypoglycemic agent (for example, glyburide) or with insulin. In these patients, careful monitoring of blood glucose is recommended. Severe cases of hypoglycemia resulting in coma or death have been reported. If a hypoglycemic reaction occurs in a patient being treated with CIPRO, discontinue CIPRO and initiate appropriate therapy immediately [see Adverse Reactions (6.1), Drug Interactions (7)].

6 ADVERSE REACTIONS

The following serious and otherwise important adverse drug reactions are discussed in greater detail in other sections of labeling:

- Disabling and Potentially Irreversible Serious Adverse Reactions [see Warnings and Precautions (5.1)]
- Tendinitis and Tendon Rupture [see Warnings and Precautions (5.2)]
- Peripheral Neuropathy [see Warnings and Precautions (5.3)]
- Central Nervous System Effects [see Warnings and Precautions (5.4)] Exacerbation of Myasthenia Gravis [see Warnings and Precautions (5.5)]
- Other Serious and Sometimes Fatal Adverse Reactions [see Warnings and Precautions (5.6)]
- Hypersensitivity Reactions [see Warnings and Precautions (5.7)]
- Hepatotoxicity [see Warnings and Precautions (5.8)]
- Risk of Aortic Aneurysm and Dissection [see Warnings and Precautions (5.9)]
- Serious Adverse Reactions with Concomitant Theophylline [see Warnings and Precautions (5.10)]
- Clostridioides difficile-Associated Diarrhea [see Warnings and Precautions (5.11)]
- Prolongation of the QT Interval [see Warnings and Precautions (5.12)]
- Musculoskeletal Disorders in Pediatric Patients [see Warnings and Precautions (5.13)]
- Photosensitivity/Phototoxicity [see Warnings and Precautions (5.14)]
- Development of Drug Resistant Bacteria [see Warnings and Precautions (5.15)]

6.1 Clinical Trials Experience

Because clinical trials are conducted under widely varying conditions, adverse reaction rates observed in the clinical trials of a drug cannot be directly compared to rates in the clinical trials of another drug and may not reflect the rates observed in practice.

Adult Patients

During clinical investigations with oral and parenteral CIPRO, 49,038 patients received courses of the drug.

The most frequently reported adverse reactions, from clinical trials of all formulations, all dosages, all drug-therapy durations, and for all indications of ciprofloxacin therapy were nausea (2.5%), diarrhea (1.6%), liver function tests abnormal (1.3%), vomiting (1%), and rash (1%).

Table 8: Medically Important Adverse Reactions That Occurred In less than 1% of Ciprofloxacin Patients
System Organ Class | Adverse Reactions
Body as a Whole | Headache; Abdominal Pain/Discomfort; Pain
Cardiovascular | Syncope; Angina Pectoris; Myocardial Infarction; Cardiopulmonary Arrest; Tachycardia; Hypotension
Central Nervous System | Restlessness; Dizziness; Insomnia; Nightmares; Hallucinations; Paranoia; Psychosis (toxic); Manic Reaction; Irritability; Tremor; Ataxia; Seizures (including Status Epilepticus); Malaise; Anorexia; Phobia; Depersonalization; Depression (potentially culminating in self-injurious behavior; (such as suicidal ideations/thoughts and attempted or completed suicide); Paresthesia; Abnormal Gait; Migraine
Gastrointestinal | Intestinal Perforation; Gastrointestinal Bleeding; Cholestatic Jaundice; Hepatitis; Pancreatitis
Hemic/Lymphatic | Petechia
Metabolic/Nutritional | Hyperglycemia; Hypoglycemia
Musculoskeletal | Arthralgia; Joint Stiffness; Muscle Weakness
Renal/Urogenital | Interstitial Nephritis; Renal Failure
Respiratory | Dyspnea; Laryngeal Edema; Hemoptysis; Bronchospasm
Skin/Hypersensitivity | Anaphylactic Reactions including life-threatening anaphylactic shock; Erythema Multiforme/Stevens-Johnson Syndrome; Exfoliative Dermatitis; Toxic Epidermal Necrolysis; Pruritus; Urticaria; Photosensitivity/Phototoxicity reaction; Flushing; Fever; Angioedema; Erythema Nodosum; Sweating
Special Senses | Blurred Vision; Disturbed Vision (chromatopsia and photopsia); Decreased Visual Acuity; Diplopia; Tinnitus; Hearing Loss; Bad Taste

In randomized, double-blind controlled clinical trials comparing CIPRO tablets [500 mg two times daily (BID)] to cefuroxime axetil (250 mg–500 mg BID) and to clarithromycin (500 mg BID) in patients with respiratory tract infections, CIPRO demonstrated a CNS adverse reaction profile comparable to the control drugs.

Pediatric Patients

Short (6 weeks) and long term (1 year) musculoskeletal and neurological safety of oral/intravenous ciprofloxacin, was compared to a cephalosporin for treatment of cUTI or pyelonephritis in pediatric patients 1 to 17 years of age (mean age of 6 ± 4 years) in an international multicenter trial. The duration of therapy was 10 to 21 days (mean duration of treatment was 11 days with a range of 1 to 88 days). A total of 335 ciprofloxacin- and 349 comparator-treated patients were enrolled.

An Independent Pediatric Safety Committee (IPSC) reviewed all cases of musculoskeletal adverse reactions including abnormal gait or abnormal joint exam (baseline or treatment-emergent). Within 6 weeks of treatment initiation, the rates of musculoskeletal adverse reactions were 9.3% (31/335) in the ciprofloxacin-treated group versus 6% (21/349) in comparator-treated patients. All musculoskeletal adverse reactions occurring by 6 weeks resolved (clinical resolution of signs and symptoms), usually within 30 days of end of treatment. Radiological evaluations were not routinely used to confirm resolution of the adverse reactions. Ciprofloxacin-treated patients were more likely to report more than one adverse reaction and on more than one occasion compared to control patients. The rate of musculoskeletal adverse reactions was consistently higher in the ciprofloxacin group compared to the control group across all age subgroups. At the end of 1 year, the rate of these adverse reactions reported at any time during that period was 13.7% (46/335) in the ciprofloxacin-treated group versus 9.5% (33/349) in the comparator-treated patients (Table 9).

Table 9: Musculoskeletal Adverse Reactions [Included: arthralgia, abnormal gait, abnormal joint exam, joint sprains, leg pain, back pain, arthrosis, bone pain, pain, myalgia, arm pain, and decreased range of motion in a joint (knee, elbow, ankle, hip, wrist, and shoulder)] as Assessed by the IPSC
 | CIPRO | Comparator
All Patients (within 6 weeks) | 31/335 (9.3%) | 21/349 (6%)
95% Confidence Interval [The study was designed to demonstrate that the arthropathy rate for the ciprofloxacin group did not exceed that of the control group by more than + 6%. At both the 6 week and 1 year evaluations, the 95% confidence interval indicated that it could not be concluded that the ciprofloxacin group had findings comparable to the control group.] | (-0.8%, +7.2%)
Age Group
12 months < 24 months | 1/36 (2.8%) | 0/41
2 years < 6 years | 5/124 (4%) | 3/118 (2.5%)
6 years < 12 years | 18/143 (12.6%) | 12/153 (7.8%)
12 years to 17 years | 7/32 (21.9%) | 6/37 (16.2 %)
All Patients (within 1 year) | 46/335 (13.7%) | 33/349 (9.5%)
95% Confidence Interval | (-0.6%, + 9.1%)

The incidence rates of neurological adverse reactions within 6 weeks of treatment initiation were 3% (9/335) in the CIPRO group versus 2% (7/349) in the comparator group and included dizziness, nervousness, insomnia, and somnolence.

In this trial, the overall incidence rates of adverse reactions within 6 weeks of treatment initiation were 41% (138/335) in the ciprofloxacin group versus 31% (109/349) in the comparator group. The most frequent adverse reactions were gastrointestinal: 15% (50/335) of ciprofloxacin patients compared to 9% (31/349) of comparator patients. Serious adverse reactions were seen in 7.5% (25/335) of ciprofloxacin-treated patients compared to 5.7% (20/349) of control patients. Discontinuation of drug due to an adverse reaction was observed in 3% (10/335) of ciprofloxacin-treated patients versus 1.4% (5/349) of comparator patients. Other adverse reactions that occurred in at least 1% of ciprofloxacin patients were diarrhea 4.8%, vomiting 4.8%, abdominal pain 3.3%, dyspepsia 2.7%, nausea 2.7%, fever 2.1%, asthma 1.8% and rash 1.8%.

Short-term safety data for ciprofloxacin was also collected in a randomized, double-blind clinical trial for the treatment of acute pulmonary exacerbations in cystic fibrosis patients (ages 5–17 years). Sixty seven patients received CIPRO IV 10 mg/kg/dose every 8 hours for one week followed by CIPRO tablets 20 mg/kg/dose every 12 hours to complete 10–21 days treatment and 62 patients received the combination of ceftazidime intravenous 50 mg/kg/dose every 8 hours and tobramycin intravenous 3 mg/kg/dose every 8 hours for a total of 10–21 days. Periodic musculoskeletal assessments were conducted by treatment-blinded examiners. Patients were followed for an average of 23 days after completing treatment (range 0–93 days). Musculoskeletal adverse reactions were reported in 22% of the patients in the ciprofloxacin group and 21% in the comparison group. Decreased range of motion was reported in 12% of the subjects in the ciprofloxacin group and 16% in the comparison group. Arthralgia was reported in 10% of the patients in the ciprofloxacin group and 11% in the comparison group. Other adverse reactions were similar in nature and frequency between treatment arms. The efficacy of CIPRO for the treatment of acute pulmonary exacerbations in pediatric cystic fibrosis patients has not been established.

In addition to the adverse reactions reported in pediatric patients in clinical trials, it should be expected that adverse reactions reported in adults during clinical trials or postmarketing experience may also occur in pediatric patients.

6.2 Postmarketing Experience

The following adverse reactions have been reported from worldwide marketing experience with fluoroquinolones, including CIPRO. Because these reactions are reported voluntarily from a population of uncertain size, it is not always possible to reliably estimate their frequency or establish a causal relationship to drug exposure (Table 10).

Table 10: Postmarketing Reports of Adverse Drug Reactions
System Organ Class | Adverse Reactions
Cardiovascular | QT prolongation; Torsade de Pointes; Vasculitis and ventricular arrhythmia; Acute myocardial ischemia with or without myocardial infarction occurring as part of an allergic reaction
Central Nervous System | Hypertonia; Myasthenia; Exacerbation of myasthenia gravis; Peripheral neuropathy; Polyneuropathy; Twitching
Eye Disorders | Nystagmus
Gastrointestinal | Pseudomembranous colitis
Hemic/Lymphatic | Pancytopenia (life threatening or fatal outcome); Methemoglobinemia
Hepatobiliary | Hepatic failure (including fatal cases)
Infections and Infestations | Candidiasis (oral, gastrointestinal, vaginal)
Investigations | Prothrombin time prolongation or decrease; Cholesterol elevation (serum); Potassium elevation (serum)
Musculoskeletal | Myalgia; Myoclonus; Tendinitis; Tendon rupture
Psychiatric Disorders | Agitation; Confusion; Delirium
Skin/Hypersensitivity | Acute generalize exanthematous pustulosis (AGEP); Fixed eruption; Serum sickness-like reaction
Special Senses | Anosmia; Hyperesthesia; Hypesthesia; Taste loss

6.3 Adverse Laboratory Changes

Changes in laboratory parameters while on CIPRO are listed below:

Hepatic –Elevations of ALT (SGPT), AST (SGOT), alkaline phosphatase, LDH, serum bilirubin.

Hematologic–Eosinophilia, leukopenia, decreased blood platelets, elevated blood platelets, pancytopenia.

Renal–Elevations of serum creatinine, BUN, crystalluria, cylindruria, and hematuria have been reported.

Other changes occurring were: elevation of serum gammaglutamyl transferase, elevation of serum amylase, reduction in blood glucose, elevated uric acid, decrease in hemoglobin, anemia, bleeding diathesis, increase in blood monocytes, and leukocytosis.

7 DRUG INTERACTIONS

Ciprofloxacin is an inhibitor of human cytochrome P450 1A2 (CYP1A2) mediated metabolism. Co-administration of CIPRO with other drugs primarily metabolized by CYP1A2 results in increased plasma concentrations of these drugs and could lead to clinically significant adverse events of the co-administered drug.

Table 11: Drugs That are Affected by and Affecting CIPRO
Drugs That are Affected by CIPRO
Drug(s) | Recommendation | Comments
Tizanidine | Contraindicated | Concomitant administration of tizanidine and CIPRO is contraindicated due to the potentiation of hypotensive and sedative effects of tizanidine [see Contraindications (4.2)]
Theophylline | Avoid Use; (Plasma Exposure Likely to be Increased and Prolonged) | Concurrent administration of CIPRO with theophylline may result in increased risk of a patient developing central nervous system (CNS) or other adverse reactions. If concomitant use cannot be avoided, monitor serum levels of theophylline and adjust dosage as appropriate [see Warnings and Precautions (5.10)].
Drugs Known to Prolong QT Interval | Avoid Use | CIPRO may further prolong the QT interval in patients receiving drugs known to prolong the QT interval (for example, class IA or III antiarrhythmics, tricyclic antidepressants, macrolides, antipsychotics) [see Warnings and Precautions (5.12) and Use in Specific Populations (8.5)].
Oral antidiabetic drugs | Use with caution; Glucose-lowering effect potentiated | Hypoglycemia sometimes severe has been reported when CIPRO and oral antidiabetic agents, mainly sulfonylureas (for example, glyburide, glimepiride), were co-administered, presumably by intensifying the action of the oral antidiabetic agent. Fatalities have been reported. Monitor blood glucose when CIPRO is co-administered with oral antidiabetic drugs [see Adverse Reactions (6.1)].
Phenytoin | Use with caution; Altered serum levels of phenytoin (increased and decreased) | To avoid the loss of seizure control associated with decreased phenytoin levels and to prevent phenytoin overdose-related adverse reactions upon CIPRO discontinuation in patients receiving both agents, monitor phenytoin therapy, including phenytoin serum concentration during and shortly after co-administration of CIPRO with phenytoin.
Cyclosporine | Use with caution; (transient elevations in serum creatinine) | Monitor renal function (in particular serum creatinine) when CIPRO is co-administered with cyclosporine.
Anti-coagulant drugs | Use with caution; (Increase in anticoagulant effect) | The risk may vary with the underlying infection, age and general status of the patient so that the contribution of CIPRO to the increase in INR (international normalized ratio) is difficult to assess. Monitor prothrombin time and INR frequently during and shortly after co-administration of CIPRO with an oral anti-coagulant (for example, warfarin).
Methotrexate | Use with caution; Inhibition of methotrexate renal tubular transport potentially leading to increased methotrexate plasma levels | Potential increase in the risk of methotrexate associated toxic reactions. Therefore, carefully monitor patients under methotrexate therapy when concomitant CIPRO therapy is indicated.
Ropinirole | Use with caution | Monitoring for ropinirole-related adverse reactions and appropriate dose adjustment of ropinirole is recommended during and shortly after co-administration with CIPRO [see Warnings and Precautions (5.16)].
Clozapine | Use with caution | Careful monitoring of clozapine associated adverse reactions and appropriate adjustment of clozapine dosage during and shortly after co-administration with CIPRO are advised.
NSAIDs | Use with caution | Non-steroidal anti-inflammatory drugs (but not acetyl salicylic acid) in combination of very high doses of quinolones have been shown to provoke convulsions in pre-clinical studies and in postmarketing.
Sildenafil | Use with caution; Two-fold increase in exposure | Monitor for sildenafil toxicity [see Clinical Pharmacology (12.3)].
Duloxetine | Avoid Use; Five-fold increase in duloxetine exposure | If unavoidable, monitor for duloxetine toxicity
Caffeine/Xanthine Derivatives | Use with caution; Reduced clearance resulting in elevated levels and prolongation of serum half-life | CIPRO inhibits the formation of paraxanthine after caffeine administration (or pentoxifylline containing products). Monitor for xanthine toxicity and adjust dose as necessary.
Zolpidem | Avoid Use | Co-administration with ciprofloxacin may increase blood levels of zolpidem, concurrent use is not recommended
Drug(s) Affecting Pharmacokinetics of CIPRO
Antacids, Sucralfate, Multivitamins and Other Products Containing Multivalent Cations (magnesium/aluminum antacids; polymeric phosphate binders (for example, sevelamer, lanthanum carbonate); sucralfate; Videx® (didanosine) chewable/buffered tablets or pediatric powder; other highly buffered drugs; or products containing calcium, iron, or zinc and dairy products) | CIPRO should be taken at least two hours before or six hours after Multivalent cation-containing products administration [see Dosage and Administration (2.4)]. | Decrease CIPRO absorption, resulting in lower serum and urine levels
Probenecid | Use with caution; (interferes with renal tubular secretion of CIPRO and increases CIPRO serum levels) | Potentiation of CIPRO toxicity may occur.

8 USE IN SPECIFIC POPULATIONS

8.1 Pregnancy

Risk Summary

Prolonged experience with ciprofloxacin in pregnant women over several decades, based on available published information from case reports, case control studies and observational studies on ciprofloxacin administered during pregnancy, have not identified any drug-associated risk of major birth defects, miscarriage or adverse maternal or fetal outcomes (see Data). Oral administration of ciprofloxacin during organogenesis at doses up to 100 mg/kg to pregnant mice and rats, and up to 30 mg/kg to pregnant rabbits did not cause fetal malformations (see Data). These doses were up to 0.3, 0.6, and 0.4 times the maximum recommended clinical oral dose in mice, rats, and rabbits, respectively, based on body surface area. The estimated background risk of major birth defects and miscarriage for the indicated population is unknown. All pregnancies have a background risk of birth defect, loss, or other adverse outcomes. In the U.S. general population, the estimated background risks of major birth defects and miscarriage in clinically recognized pregnancies is 2 to 4% and 15 to 20%, respectively.

Data

Human Data

While available studies cannot definitively establish the absence of risk, published data from prospective observational studies over several decades have not established an association with ciprofloxacin use during pregnancy and major birth defects, miscarriage, or adverse maternal or fetal outcomes. Available studies have methodological limitations including small sample size and some of them are not specific for ciprofloxacin. A controlled prospective observational study followed 200 women exposed to fluoroquinolones (52.5% exposed to ciprofloxacin and 68% first trimester exposures) during gestation. In utero exposure to fluoroquinolones during embryogenesis was not associated with increased risk of major malformations. The reported rates of major congenital malformations were 2.2% for the fluoroquinolone group and 2.6% for the control group (background incidence of major malformations is 1–5%). Rates of spontaneous abortions, prematurity and low birth weight did not differ between the groups and there were no clinically significant musculoskeletal dysfunctions up to one year of age in the ciprofloxacin exposed children.

Another prospective follow-up study reported on 549 pregnancies with fluoroquinolone exposure (93% first trimester exposures). There were 70 ciprofloxacin exposures, all within the first trimester. The malformation rates among live-born babies exposed to ciprofloxacin and to fluoroquinolones overall were both within background incidence ranges. No specific patterns of congenital abnormalities were found. The study did not reveal any clear adverse reactions due to in utero exposure to ciprofloxacin.

No differences in the rates of prematurity, spontaneous abortions, or birth weight were seen in women exposed to ciprofloxacin during pregnancy. However, these small postmarketing epidemiology studies, of which most experience is from short term, first trimester exposure, are insufficient to evaluate the risk for less common defects or to permit reliable and definitive conclusions regarding the safety of ciprofloxacin in pregnant women and their developing fetuses.

Animal Data

Developmental toxicology studies have been performed with ciprofloxacin in rats, mice, and rabbits. In rats and mice, oral doses up to 100 mg/kg administered during organogenesis (Gestation Days, GD, 6-17) were not associated with adverse developmental outcomes, including embryofetal toxicity or malformations. In rats and mice, a 100 mg/kg dose is approximately 0.6 and 0.3 times the maximum daily human oral dose (1500 mg/day) based upon body surface area, respectively. In a series of rabbit developmental toxicology studies, does received oral or intravenous ciprofloxacin for one of the following 5 day periods: GD 6 to 10, GD 10 to 14, or GD 14 to 18, intended to cover the period of organogenesis. This was an attempt to mitigate the gastrointestinal intolerance observed in rabbits that receive antibacterials manifested by reduced maternal food consumption and weight loss, that can lead to embryofetal resorption or spontaneous abortion. An oral ciprofloxacin dose of 100 mg/kg (approximately 1.3 times the highest recommended clinical oral dose based on body surface area) caused excessive maternal toxicity confounding evaluation of the fetuses. A 30 mg/kg oral dose (approximately 0.4 times the highest recommended clinical oral dose) was associated with suppression of maternal and fetal body weight gain, but fetal malformations were not observed. Intravenous administration of doses up to 20 mg/kg (approximately 0.3 times the highest recommended clinical oral dose based upon body surface area) to pregnant rabbits was not maternally toxic and neither embryofetal toxicity nor fetal malformations were observed.

In peri- and post-natal studies, rats received ciprofloxacin doses up to 200 mg/kg/day (oral) or up to 30 mg/kg/day (subcutaneous) from GD 16 to 22 days postpartum. The 200 mg/kg dose is approximately 1.3-times the maximum recommended clinical oral dose based on body surface area. Neither maternal toxicity nor adverse effects on growth and development of the pups were observed, including no sign of arthropathy on the rear leg joints of the pups. Ciprofloxacin and other quinolones have been shown to cause arthropathy in immature animals of most species tested when administered directly [see Warnings and Precautions (5.13) and Nonclinical Toxicology 13.2].

8.2 Lactation

Risk Summary

Published literature reports that ciprofloxacin is present in human milk following intravenous and oral administration. There is no information regarding effects of CIPRO on milk production or the breastfed infant. Because of the potential risk of serious adverse reactions in breastfed infants, including arthropathy shown in juvenile animal studies [see Use in Specific Populations (8.4), (Clinical Considerations)], for most indications a lactating woman may consider pumping and discarding breast milk during treatment with CIPRO and an additional two days (five half-lives) after the last dose. Alternatively, advise a woman that breastfeeding is not recommended during treatment with CIPRO and for an additional two days (five half-lives) after the last dose.

However, for inhalation anthrax (post exposure), during an incident resulting in exposure to anthrax, the risk-benefit assessment of continuing breastfeeding while the mother (and potentially the infant) is (are) on CIPRO may be acceptable [see Dosage and Administration (2.2), Pediatric Use (8.4), and Clinical Studies (14.2)]. The developmental and health benefits of breastfeeding should be considered along with the mother’s clinical need for CIPRO and any potential adverse effects on the breastfed child from CIPRO or from the underlying maternal condition.

Clinical Considerations

Ciprofloxacin may cause intestinal flora alteration of the breastfeeding infant. Advise a woman to monitor the breastfed infant for loose or bloody stools and candidiasis (thrush, diaper rash).

8.4 Pediatric Use

Although effective in clinical trials, CIPRO is not a drug of first choice in the pediatric population due to an increased incidence of adverse reactions compared to controls. Quinolones, including CIPRO, cause arthropathy (arthralgia, arthritis), in juvenile animals [see Warnings and Precautions (5.13) and Nonclinical Toxicology (13.2)].

Complicated Urinary Tract Infection and Pyelonephritis

CIPRO is indicated for the treatment of cUTI and pyelonephritis due to Escherichia coli in pediatric patients 1 to 17 years of age. Although effective in clinical trials, CIPRO is not a drug of first choice in the pediatric population due to an increased incidence of adverse reactions compared to the controls, including events related to joints and/or surrounding tissues [see Adverse Reactions (6.1) and Clinical Studies (14.1)].

Inhalational Anthrax (Post-Exposure)

CIPRO is indicated in pediatric patients from birth to 17 years of age, for inhalational anthrax (post-exposure). The risk-benefit assessment indicates that administration of ciprofloxacin to pediatric patients is appropriate [see Dosage and Administration (2.2) and Clinical Studies (14.2)].

Plague

CIPRO is indicated in pediatric patients from birth to 17 years of age, for treatment of plague, including pneumonic and septicemic plague due to Yersinia pestis (Y. pestis) and prophylaxis for plague. Efficacy studies of CIPRO could not be conducted in humans with pneumonic plague for feasibility reasons. Therefore, approval of this indication was based on an efficacy study conducted in animals. The risk-benefit assessment indicates that administration of CIPRO to pediatric patients is appropriate [see Indications and Usage (1.8), Dosage and Administration (2.2) and Clinical Studies (14.3)].

8.5 Geriatric Use

Geriatric patients are at increased risk for developing severe tendon disorders including tendon rupture when being treated with a fluoroquinolone such as CIPRO. This risk is further increased in patients receiving concomitant corticosteroid therapy. Tendinitis or tendon rupture can involve the Achilles, hand, shoulder, or other tendon sites and can occur during or after completion of therapy; cases occurring up to several months after fluoroquinolone treatment have been reported. Caution should be used when prescribing CIPRO to elderly patients especially those on corticosteroids. Patients should be informed of this potential adverse reaction and advised to discontinue CIPRO and contact their healthcare provider if any symptoms of tendinitis or tendon rupture occur. [see Boxed Warning, Warnings and Precautions (5.2), and Adverse Reactions (6.2)].

Epidemiologic studies report an increased rate of aortic aneurysm and dissection within two months following use of fluoroquinolones, particularly in elderly patients [see Warnings and Precautions (5.9)].

In a retrospective analysis of 23 multiple-dose controlled clinical trials of CIPRO encompassing over 3500 ciprofloxacin-treated patients, 25% of patients were greater than or equal to 65 years of age and 10% were greater than or equal to 75 years of age. No overall differences in safety or effectiveness were observed between these subjects and younger subjects, and other reported clinical experience has not identified differences in responses between the elderly and younger patients, but greater sensitivity of some older individuals on any drug therapy cannot be ruled out. Ciprofloxacin is known to be substantially excreted by the kidney, and the risk of adverse reactions may be greater in patients with impaired renal function. No alteration of dosage is necessary for patients greater than 65 years of age with normal renal function. However, since some older individuals experience reduced renal function by virtue of their advanced age, care should be taken in dose selection for elderly patients, and renal function monitoring may be useful in these patients [see Dosage and Administration (2.3) and Clinical Pharmacology (12.3)].

In general, elderly patients may be more susceptible to drug-associated effects on the QT interval. Therefore, precaution should be taken when using CIPRO with concomitant drugs that can result in prolongation of the QT interval (for example, class IA or class III antiarrhythmics) or in patients with risk factors for torsade de pointes (for example, known QT prolongation, uncorrected hypokalemia) [see Warnings and Precautions (5.12)].

8.6 Renal Impairment

Ciprofloxacin is eliminated primarily by renal excretion; however, the drug is also metabolized and partially cleared through the biliary system of the liver and through the intestine. These alternative pathways of drug elimination appear to compensate for the reduced renal excretion in patients with renal impairment. Nonetheless, some modification of dosage is recommended, particularly for patients with severe renal dysfunction [see Dosage and Administration (2.3) and Clinical Pharmacology (12.3)].

8.7 Hepatic Impairment

In preliminary studies in patients with stable chronic liver cirrhosis, no significant changes in ciprofloxacin pharmacokinetics have been observed. The pharmacokinetics of ciprofloxacin in patients with acute hepatic insufficiency, have not been studied.

10 OVERDOSAGE

In the event of acute overdosage, reversible renal toxicity has been reported in some cases. Empty the stomach by inducing vomiting or by gastric lavage. Observe the patient carefully and give supportive treatment, including monitoring of renal function, urinary pH and acidify, if required, to prevent crystalluria and administration of magnesium, aluminum, or calcium containing antacids which can reduce the absorption of ciprofloxacin. Adequate hydration must be maintained. Only a small amount of ciprofloxacin (less than 10%) is removed from the body after hemodialysis or peritoneal dialysis.

11 DESCRIPTION

CIPRO (ciprofloxacin hydrochloride) Tablets and CIPRO (ciprofloxacin) Oral Suspension are synthetic antimicrobial agents for oral administration. Ciprofloxacin hydrochloride, USP, a fluoroquinolone, is the monohydrochloride monohydrate salt of 1-cyclopropyl-6-fluoro-1, 4-dihydro-4-oxo-7-(1-piperazinyl)-3-quinolinecarboxylic acid. It is a faintly yellowish to light yellow crystalline substance with a molecular weight of 385.8. Its empirical formula is C17H18FN3O3•HCl•H2O and its chemical structure is as follows:

Ciprofloxacin is 1-cyclopropyl-6-fluoro-1,4-dihydro-4-oxo-7-(1-piperazinyl)-3-quinolinecarboxylic acid. Its empirical formula is C17H18FN3O3 and its molecular weight is 331.4. It is a faintly yellowish to light yellow crystalline substance and its chemical structure is as follows:

CIPRO film-coated tablets are available in 250 mg and 500 mg (ciprofloxacin equivalent) strengths. Each CIPRO film-coated tablet contains 250 mg (equivalent to 291 mg ciprofloxacin hydrochloride monohydrate) or 500 mg of ciprofloxacin (equivalent to 582 mg ciprofloxacin hydrochloride monohydrate) CIPRO tablets are white to slightly yellowish. The inactive ingredients are cornstarch, crospovidone, hypromellose, magnesium stearate, microcrystalline cellulose, polyethylene glycol, silicon dioxide, and titanium dioxide.

CIPRO Oral Suspension is available in 5% (5 g ciprofloxacin in 100 mL) and 10% (10 g ciprofloxacin in 100 mL) strengths. CIPRO Oral Suspension is a white to slightly yellowish suspension with strawberry flavor which may contain yellow-orange droplets. It is composed of ciprofloxacin microcapsules and diluent which are mixed prior to dispensing [see Dosage and Administration (2.5)]. The components of the suspension have the following compositions:

- Microcapsules–ciprofloxacin, hypromellose, magnesium stearate, methacrylic acid copolymer, Polysorbate 20 and povidone.
- Diluent–medium-chain triglycerides, sucrose, soy-lecithin, water, and strawberry flavor.
- Five (5) mL of 5% suspension contains approximately 1.4 g of sucrose and 5 mL of 10% suspension contains approximately 1.3 g of sucrose.

12 CLINICAL PHARMACOLOGY

12.1 Mechanism of Action

Ciprofloxacin is a member of the fluoroquinolone class of antibacterial agents [see Microbiology (12.4)].

12.3 Pharmacokinetics

Absorption

The absolute bioavailability of ciprofloxacin when given as an oral tablet is approximately 70% with no substantial loss by first pass metabolism. Ciprofloxacin maximum serum concentrations (Cmax) and area under the curve (AUC) are shown in the chart for the 250 mg to 1000 mg dose range (Table 12).

Table 12: Ciprofloxacin Cmax and AUC Following Administration of Single Doses of CIPRO Tablets to Healthy Subjects
Dose (mg) | Cmax (mcg/mL) | AUC (mcg•hr/mL)
250 | 1.2 | 4.8
500 | 2.4 | 11.6
750 | 4.3 | 20.2
1000 | 5.4 | 30.8

Maximum serum concentrations are attained 1 to 2 hours after oral dosing. Mean concentrations 12 hours after dosing with 250, 500, or 750 mg are 0.1, 0.2, and 0.4 mcg/mL, respectively. The serum elimination half-life in subjects with normal renal function is approximately 4 hours. Serum concentrations increase proportionately with doses up to 1000 mg.

A 500 mg oral dose given every 12 hours has been shown to produce an AUC equivalent to that produced by an intravenous infusion of 400 mg CIPRO given over 60 minutes every 12 hours. A 750 mg oral dose given every 12 hours has been shown to produce an AUC at steady-state equivalent to that produced by an intravenous infusion of 400 mg given over 60 minutes every 8 hours. A 750 mg oral dose results in a Cmax similar to that observed with a 400 mg intravenous dose (Table 13). A 250 mg oral dose given every 12 hours produces an AUC equivalent to that produced by an infusion of 200 mg CIPRO given every 12 hours.

Table 13: Steady-state Pharmacokinetic Parameters Following Multiple Oral and Intravenous Doses (Adults)
Parameters | 500 mg | 400 mg | 750 mg | 400 mg
 | every 12 hours, orally | every 12 hours, intravenously | every 12 hours, orally | every 8 hours, intravenously
AUC0-24h,ss (µg•h/mL) | 27.4 [AUC0-12h x 2] | 25.4 | 31.6 | 32.9 [AUC0-8h x 3]
Cmax,ss (µg/mL) | 2.97 | 4.56 | 3.59 | 4.07

Food

When CIPRO Tablet is given concomitantly with food, there is a delay in the absorption of the drug, resulting in peak concentrations that occur closer to 2 hours after dosing rather than 1 hour whereas there is no delay observed when CIPRO Suspension is given with food. The overall absorption of CIPRO Tablet or CIPRO Suspension, however, is not substantially affected. The pharmacokinetics of ciprofloxacin given as the suspension are also not affected by food. Avoid concomitant administration of CIPRO with dairy products (like milk or yogurt) or calcium-fortified juices alone since decreased absorption is possible; however, CIPRO may be taken with a meal that contains these products

With oral administration, a 500 mg dose, given as 10 mL of the 5% CIPRO Suspension (containing 250 mg ciprofloxacin/5mL) is bioequivalent to the 500 mg tablet. A 10 mL volume of the 5% CIPRO Suspension (containing 250 mg ciprofloxacin/5mL) is bioequivalent to a 5 mL volume of the 10% CIPRO Suspension (containing 500 mg ciprofloxacin/5mL).

Distribution

The binding of ciprofloxacin to serum proteins is 20% to 40% which is not likely to be high enough to cause significant protein binding interactions with other drugs.

After oral administration, ciprofloxacin is widely distributed throughout the body. Tissue concentrations often exceed serum concentrations in both men and women, particularly in genital tissue including the prostate. Ciprofloxacin is present in active form in the saliva, nasal and bronchial secretions, mucosa of the sinuses, sputum, skin blister fluid, lymph, peritoneal fluid, bile, and prostatic secretions. Ciprofloxacin has also been detected in lung, skin, fat, muscle, cartilage, and bone. The drug diffuses into the cerebrospinal fluid (CSF); however, CSF concentrations are generally less than 10% of peak serum concentrations. Low levels of the drug have been detected in the aqueous and vitreous humors of the eye.

Metabolism

Four metabolites have been identified in human urine which together account for approximately 15% of an oral dose. The metabolites have antimicrobial activity, but are less active than unchanged ciprofloxacin. Ciprofloxacin is an inhibitor of human cytochrome P450 1A2 (CYP1A2) mediated metabolism. Co-administration of ciprofloxacin with other drugs primarily metabolized by CYP1A2 results in increased plasma concentrations of these drugs and could lead to clinically significant adverse events of the co-administered drug [see Contraindications (4.2), Warnings and Precautions (5.10, 5.16), and Drug Interactions (7)].

Excretion

The serum elimination half-life in subjects with normal renal function is approximately 4 hours. Approximately 40 to 50% of an orally administered dose is excreted in the urine as unchanged drug. After a 250 mg oral dose, urine concentrations of ciprofloxacin usually exceed 200 mcg/mL during the first two hours and are approximately 30 mcg/mL at 8 to 12 hours after dosing. The urinary excretion of ciprofloxacin is virtually complete within 24 hours after dosing. The renal clearance of ciprofloxacin, which is approximately 300 mL/minute, exceeds the normal glomerular filtration rate of 120 mL/minute. Thus, active tubular secretion would seem to play a significant role in its elimination. Co-administration of probenecid with ciprofloxacin results in about a 50% reduction in the ciprofloxacin renal clearance and a 50% increase in its concentration in the systemic circulation.

Although bile concentrations of ciprofloxacin are several fold higher than serum concentrations after oral dosing, only a small amount of the dose administered is recovered from the bile as unchanged drug. An additional 1% to 2% of the dose is recovered from the bile in the form of metabolites. Approximately 20% to 35% of an oral dose is recovered from the feces within 5 days after dosing. This may arise from either biliary clearance or transintestinal elimination.

Specific Populations

Elderly

Pharmacokinetic studies of the oral (single dose) and intravenous (single and multiple dose) forms of ciprofloxacin indicate that plasma concentrations of ciprofloxacin are higher in elderly subjects (older than 65 years) as compared to young adults. Although the Cmax is increased 16% to 40%, the increase in mean AUC is approximately 30%, and can be at least partially attributed to decreased renal clearance in the elderly. Elimination half-life is only slightly (~20%) prolonged in the elderly. These differences are not considered clinically significant [see Use in Specific Populations (8.5)].

Renal Impairment

In patients with reduced renal function, the half-life of ciprofloxacin is slightly prolonged. Dosage adjustments may be required [see Use in Specific Populations (8.6) and Dosage and Administration (2.3)].

Hepatic Impairment

In preliminary studies in patients with stable chronic liver cirrhosis, no significant changes in ciprofloxacin pharmacokinetics have been observed. The kinetics of ciprofloxacin in patients with acute hepatic insufficiency, have not been fully studied.

Pediatrics

Table 14 summarizes pharmacokinetic parameters in pediatric patients aged less than 1 to less than 12 years of age receiving intravenous treatment.

Table 14: Estimated AUC0–24,ss and Cmax,ss for Intravenous Treatment (1-h infusion) in Pediatric Patients Following a Multiple Dosing Regimen of 10 mg/kg, Three Times Daily
Age | AUC0–24,ss (mg h/L) | Cmax,ss (mg/L)
Less than1 year | 30.9 [3 x AUC0–8,ss] | 2.8
1 to less than 2 years | 27.8 | 3.6
2 to less than 6 years | 28.9 | 2.7
6 to less than 12 years | 20.4 | 2.0

These values are within the range reported for adults at therapeutic doses. Based on population pharmacokinetic analysis of pediatric patients with various infections, the predicted mean half-life in children is approximately 4 hours –5 hours, and the bioavailability of the oral suspension is approximately 60%.

Drug-Drug Interactions

Antacids

Concurrent administration of antacids containing magnesium hydroxide or aluminum hydroxide may reduce the bioavailability of ciprofloxacin by as much as 90% [see Dosage and Administration (2.4) and Drug Interactions (7)].

Histamine H2-receptor antagonists

Histamine H2-receptor antagonists appear to have no significant effect on the bioavailability of ciprofloxacin.

Metronidazole

The serum concentrations of ciprofloxacin and metronidazole were not altered when these two drugs were given concomitantly.

Tizanidine

In a pharmacokinetic study, systemic exposure of tizanidine (4 mg single dose) was significantly increased (Cmax 7-fold, AUC 10-fold) when the drug was given concomitantly with CIPRO (500 mg twice a day for 3 days). Concomitant administration of tizanidine and CIPRO is contraindicated due to the potentiation of hypotensive and sedative effects of tizanidine [see Contraindications (4.2)].

Ropinirole

In a study conducted in 12 patients with Parkinson’s disease who were administered 6 mg ropinirole once daily with 500 mg CIPRO twice-daily, the mean Cmax and mean AUC of ropinirole were increased by 60% and 84%, respectively. Monitoring for ropinirole-related adverse reactions and appropriate dose adjustment of ropinirole is recommended during and shortly after co-administration with CIPRO [see Warnings and Precautions (5.10)].

Clozapine

Following concomitant administration of 250 mg CIPRO with 304 mg clozapine for 7 days, serum concentrations of clozapine and N-desmethylclozapine were increased by 29% and 31%, respectively. Careful monitoring of clozapine associated adverse reactions and appropriate adjustment of clozapine dosage during and shortly after co-administration with CIPRO are advised.

Sildenafil

Following concomitant administration of a single oral dose of 50 mg sildenafil with 500 mg CIPRO to healthy subjects, the mean Cmax and mean AUC of sildenafil were both increased approximately two-fold. Use sildenafil with caution when co-administered with CIPRO due to the expected two-fold increase in the exposure of sildenafil upon co-administration of CIPRO.

Duloxetine

In clinical studies it was demonstrated that concomitant use of duloxetine with strong inhibitors of the CYP450 1A2 isozyme such as fluvoxamine, may result in a 5-fold increase in mean AUC and a 2.5-fold increase in mean Cmax of duloxetine.

Lidocaine

In a study conducted in 9 healthy volunteers, concomitant use of 1.5 mg/kg IV lidocaine with CIPRO 500 mg twice daily resulted in an increase of lidocaine Cmax and AUC by 12% and 26%, respectively. Although lidocaine treatment was well tolerated at this elevated exposure, a possible interaction with CIPRO and an increase in adverse reactions related to lidocaine may occur upon concomitant administration.

Metoclopramide

Metoclopramide significantly accelerates the absorption of oral ciprofloxacin resulting in a shorter time to reach maximum plasma concentrations. No significant effect was observed on the bioavailability of ciprofloxacin.

Omeprazole

When CIPRO was administered as a single 1000 mg dose concomitantly with omeprazole (40 mg once daily for three days) to 18 healthy volunteers, the mean AUC and Cmax of ciprofloxacin were reduced by 20% and 23%, respectively. The clinical significance of this interaction has not been determined.

12.4 Microbiology

Mechanism of Action

The bactericidal action of ciprofloxacin results from inhibition of the enzymes topoisomerase II (DNA gyrase) and topoisomerase IV (both Type II topoisomerases), which are required for bacterial DNA replication, transcription, repair, and recombination.

Mechanism of Resistance

The mechanism of action of fluoroquinolones, including ciprofloxacin, is different from that of penicillins, cephalosporins, aminoglycosides, macrolides, and tetracyclines; therefore, microorganisms resistant to these classes of drugs may be susceptible to ciprofloxacin. Resistance to fluoroquinolones occurs primarily by either mutations in the DNA gyrases, decreased outer membrane permeability, or drug efflux. In vitro resistance to ciprofloxacin develops slowly by multiple step mutations. Resistance to ciprofloxacin due to spontaneous mutations occurs at a general frequency of between < 10^-9 to 1x10^-6.

Cross Resistance

There is no known cross-resistance between ciprofloxacin and other classes of antimicrobials.

Ciprofloxacin has been shown to be active against most isolates of the following bacteria, both in vitro and in clinical infections [see Indications and Usage (1)].

Gram-positive bacteria

Bacillus anthracis

Enterococcus faecalis

Staphylococcus aureus (methicillin-susceptible isolates only)

Staphylococcus epidermidis (methicillin-susceptible isolates only)

Staphylococcus saprophyticus

Streptococcus pneumoniae

Streptococcus pyogenes

Gram-negative bacteria

Campylobacter jejuni

Citrobacter koseri

Citrobacter freundii

Enterobacter cloacae

Escherichia coli

Haemophilus influenzae

Haemophilus parainfluenzae

Klebsiella pneumoniae

Moraxella catarrhalis

Morganella morganii

Neisseria gonorrhoeae

Proteus mirabilis

Proteus vulgaris

Providencia rettgeri

Providencia stuartii

Pseudomonas aeruginosa

Salmonella typhi

Serratia marcescens

Shigella boydii

Shigella dysenteriae

Shigella flexneri

Shigella sonnei

Yersinia pestis

The following in vitro data are available, but their clinical significance is unknown. At least 90 percent of the following bacteria exhibit an in vitro minimum inhibitory concentration (MIC) less than or equal to the susceptible breakpoint for ciprofloxacin against isolates of similar genus or organism group. However, the efficacy of ciprofloxacin in treating clinical infections caused by these bacteria has not been established in adequate and well-controlled clinical trials.

Gram-positive bacteria

Staphylococcus haemolyticus (methicillin-susceptible isolates only)

Staphylococcus hominis (methicillin-susceptible isolates only)

Gram-negative bacteria

Acinetobacter lwoffi

Aeromonas hydrophila

Edwardsiella tarda

Enterobacter aerogenes

Klebsiella oxytoca

Legionella pneumophila

Pasteurella multocida

Salmonella enteritidis

Vibrio cholerae

Vibrio parahaemolyticus

Vibrio vulnificus

Yersinia enterocolitica

Susceptibility Testing

For specific information regarding susceptibility test interpretive criteria and associated test methods and quality control standards recognized by FDA for this drug, please see: https://www.fda.gov/STIC.

13 NONCLINICAL TOXICOLOGY

13.1 Carcinogenesis, Mutagenesis, Impairment of Fertility

Eight in vitro mutagenicity tests have been conducted with ciprofloxacin, and the test results are listed below:

- Salmonella/Microsome Test (Negative)
- E. coli DNA Repair Assay (Negative)
- Mouse Lymphoma Cell Forward Mutation Assay (Positive)
- Chinese Hamster V79 Cell HGPRT Test (Negative)
- Syrian Hamster Embryo Cell Transformation Assay (Negative)
- Saccharomyces cerevisiae Point Mutation Assay (Negative)
- Saccharomyces cerevisiae Mitotic Crossover and Gene Conversion Assay (Negative)
- Rat Hepatocyte DNA Repair Assay (Positive)
- Thus, 2 of the 8 tests were positive, but results of the following 3 in vivo test systems gave negative results:
- Rat Hepatocyte DNA Repair Assay
- Micronucleus Test (Mice)
- Dominant Lethal Test (Mice)

Long-term carcinogenicity studies in rats and mice resulted in no carcinogenic or tumorigenic effects due to ciprofloxacin at daily oral dose levels up to 250 mg/kg and 750 mg/kg to rats and mice, respectively (approximately 1.7- and 2.5- times the highest recommended therapeutic dose based upon body surface area, respectively).

Results from photo co-carcinogenicity testing indicate that ciprofloxacin does not reduce the time to appearance of UV-induced skin tumors as compared to vehicle control. Hairless (Skh-1) mice were exposed to UVA light for 3.5 hours five times every two weeks for up to 78 weeks while concurrently being administered ciprofloxacin. The time to development of the first skin tumors was 50 weeks in mice treated concomitantly with UVA and ciprofloxacin (mouse dose approximately equal to maximum recommended human dose based upon body surface area), as opposed to 34 weeks when animals were treated with both UVA and vehicle. The times to development of skin tumors ranged from 16 weeks to 32 weeks in mice treated concomitantly with UVA and other quinolones.^5

In this model, mice treated with ciprofloxacin alone did not develop skin or systemic tumors. There are no data from similar models using pigmented mice and/or fully haired mice. The clinical significance of these findings to humans is unknown.

Fertility studies performed in male and female rats at oral doses of ciprofloxacin up to 100 mg/kg (approximately 0.6-times the highest recommended therapeutic oral dose based upon body surface area) revealed no evidence of impairment. Male rats received oral ciprofloxacin for 10 weeks prior to mating and females were dosed for 3 weeks prior to mating through Gestation Day 7.

13.2 Animal Toxicology and/or Pharmacology

Ciprofloxacin and other quinolones have been shown to cause arthropathy in immature animals of most species tested [see Warnings and Precautions (5.13)]. Damage of weight bearing joints was observed in juvenile dogs and rats. In young beagles, 100 mg/kg ciprofloxacin, given daily for 4 weeks, caused degenerative articular changes of the knee joint. At 30 mg/kg, the effect on the joint was minimal. In a subsequent study in young beagle dogs, oral ciprofloxacin doses of 30 mg/kg and 90 mg/kg ciprofloxacin (approximately 1.3-times and 3.5-times the pediatric dose based upon comparative plasma AUCs) given daily for 2 weeks caused articular changes which were still observed by histopathology after a treatment-free period of 5 months. At 10 mg/kg (approximately 0.6-times the pediatric dose based upon comparative plasma AUCs), no effects on joints were observed. This dose was also not associated with arthrotoxicity after an additional treatment-free period of 5 months. In another study, removal of weight bearing from the joint reduced the lesions but did not totally prevent them.

Crystalluria, sometimes associated with secondary nephropathy, occurs in laboratory animals dosed with ciprofloxacin. This is primarily related to the reduced solubility of ciprofloxacin under alkaline conditions, which predominate in the urine of test animals; in man, crystalluria is rare since human urine is typically acidic. In rhesus monkeys, crystalluria without nephropathy was noted after single oral doses as low as 5 mg/kg. (approximately 0.07-times the highest recommended therapeutic dose based upon body surface area). After 6 months of intravenous dosing at 10 mg/kg/day, no nephropathological changes were noted; however, nephropathy was observed after dosing at 20 mg/kg/day for the same duration (approximately 0.2-times the highest recommended therapeutic dose based upon body surface area).

In dogs, ciprofloxacin at 3 mg/kg and 10 mg/kg by rapid intravenous injection (15 sec.) produces pronounced hypotensive effects. These effects are considered to be related to histamine release, since they are partially antagonized by pyrilamine, an antihistamine. In rhesus monkeys, rapid intravenous injection also produces hypotension but the effect in this species is inconsistent and less pronounced.

In mice, concomitant administration of nonsteroidal anti-inflammatory drugs such as phenylbutazone and indomethacin with quinolones has been reported to enhance the CNS stimulatory effect of quinolones.

Ocular toxicity seen with some related drugs has not been observed in ciprofloxacin-treated animals

14 CLINICAL STUDIES

14.1 Complicated Urinary Tract Infection and Pyelonephritis–Efficacy in Pediatric Patients

CIPRO administered intravenously and/or orally was compared to a cephalosporin for treatment of cUTI and pyelonephritis in pediatric patients 1 to 17 years of age (mean age of 6 ± 4 years). The trial was conducted in the US, Canada, Argentina, Peru, Costa Rica, Mexico, South Africa, and Germany. The duration of therapy was 10 to 21 days (mean duration of treatment was 11 days with a range of 1 to 88 days). The primary objective of the study was to assess musculoskeletal and neurological safety.

Patients were evaluated for clinical success and bacteriological eradication of the baseline organism(s) with no new infection or superinfection at 5 to 9 days post-therapy (Test of Cure or TOC). The Per Protocol population had a causative organism(s) with protocol specified colony count(s) at baseline, no protocol violation, and no premature discontinuation or loss to follow-up (among other criteria).

The clinical success and bacteriologic eradication rates in the Per Protocol population were similar between CIPRO and the comparator group as shown below.

Table 15: Clinical Success and Bacteriologic Eradication at Test of Cure (5 to 9 Days Post-Therapy)
 | CIPRO | Comparator
Randomized Patients | 337 | 352
Per Protocol Patients | 211 | 231
Clinical Response at 5 to 9 Days Post-Treatment | 95.7% (202/211) | 92.6% (214/231)
 | 95% CI [-1.3%, 7.3%]
Bacteriologic Eradication by Patient at 5 to 9 Days Post-Treatment [Patients with baseline pathogen(s) eradicated and no new infections or superinfections/total number of patients. There were 5.5% (6/211) ciprofloxacin and 9.5% (22/231) comparator patients with superinfections or new infections.] | 84.4% (178/211) | 78.3% (181/231)
 | 95% CI [-1.3%, 13.1%]
Bacteriologic Eradication of the Baseline Pathogen at 5 to 9 Days Post-Treatment
Escherichia coli | 156/178 (88%) | 161/179 (90%)

14.2 Inhalational Anthrax in Adults and Pediatrics

The mean serum concentrations of ciprofloxacin associated with a statistically significant improvement in survival in the rhesus monkey model of inhalational anthrax are reached or exceeded in adult and pediatric patients receiving oral and intravenous regimens. Ciprofloxacin pharmacokinetics have been evaluated in various human populations. The mean peak serum concentration achieved at steady-state in human adults receiving 500 mg orally every 12 hours is 2.97 mcg/mL, and 4.56 mcg/mL following 400 mg intravenously every 12 hours. The mean trough serum concentration at steady-state for both of these regimens is 0.2 mcg/mL. In a study of 10 pediatric patients between 6 and 16 years of age, the mean peak plasma concentration achieved is 8.3 mcg/mL and trough concentrations range from 0.09 mcg/mL to 0.26 mcg/mL, following two 30-minute intravenous infusions of 10 mg/kg administered 12 hours apart. After the second intravenous infusion patients switched to 15 mg/kg orally every 12 hours achieve a mean peak concentration of 3.6 mcg/mL after the initial oral dose. Long-term safety data, including effects on cartilage, following the administration of CIPRO to pediatric patients are limited. Ciprofloxacin serum concentrations achieved in humans serve as a surrogate endpoint reasonably likely to predict clinical benefit and provide the basis for this indication.^1

A placebo-controlled animal study in rhesus monkeys exposed to an inhaled mean dose of 11 LD50 (~5.5 x 10^5 spores (range 5–30 LD50) of B. anthracis was conducted. The minimal inhibitory concentration (MIC) of ciprofloxacin for the anthrax strain used in this study was 0.08 mcg/mL. In the animals studied, mean serum concentrations of ciprofloxacin achieved at expected Tmax (1 hour post-dose) following oral dosing to steady-state ranged from 0.98 mcg/mL to 1.69 mcg/mL. Mean steady-state trough concentrations at 12 hours post-dose ranged from 0.12 mcg/mL to 0.19 mcg/mL.^6 Mortality due to anthrax for animals that received a 30-day regimen of oral ciprofloxacin beginning 24 hours post-exposure was significantly lower (1/9), compared to the placebo group (9/10) [p= 0.001]. The one CIPRO-treated animal that died of anthrax did so following the 30-day drug administration period.^7

More than 9300 persons were recommended to complete a minimum of 60 days of antibacterial prophylaxis against possible inhalational exposure to B. anthracis during 2001. CIPRO was recommended to most of those individuals for all or part of the prophylaxis regimen. Some persons were also given anthrax vaccine or were switched to alternative antibacterial drugs. No one who received CIPRO or other therapies as prophylactic treatment subsequently developed inhalational anthrax. The number of persons who received CIPRO as all or part of their post-exposure prophylaxis regimen is unknown.

14.3 Plague

A placebo-controlled animal study in African green monkeys exposed to an inhaled mean dose of 110 LD50 (range 92 to 127 LD50) of Yersinia pestis (CO92 strain) was conducted. The minimal inhibitory concentration (MIC) of ciprofloxacin for the Y. pestis strain used in this study was 0.015 mcg/mL. Mean peak serum concentrations of ciprofloxacin achieved at the end of a single 60 minute infusion were 3.49 ± mcg/mL 0.55 mcg/mL, 3.91 mcg/mL ± 0.58 mcg/mL and 4.03 mcg/mL ± 1.22 mcg/mL on Day 2, Day 6 and Day 10 of treatment in African green monkeys, respectively All trough concentrations (Day 2, Day 6 and Day 10) were <0.5 mcg /mL. Animals were randomized to receive either a 10-day regimen of intravenous ciprofloxacin 15 mg/kg, or placebo beginning when animals were found to be febrile (a body temperature greater than 1.5oC over baseline for two hours), or at 76 hours post-challenge, whichever occurred sooner. Mortality in the ciprofloxacin group was significantly lower (1/10) compared to the placebo group (2/2) [difference: -90.0%, 95% exact confidence interval: -99.8% to -5.8%]. The one ciprofloxacin-treated animal that died did not receive the proposed dose of ciprofloxacin due to a failure of the administration catheter. Circulating ciprofloxacin concentration was below 0.5 mcg/mL at all timepoints tested in this animal. It became culture negative on Day 2 of treatment, but had a resurgence of low grade bacteremia on Day 6 after treatment initiation. Terminal blood culture in this animal was negative.^8

15 REFERENCES

1. 21 CFR 314.510 (Subpart H–Accelerated Approval of New Drugs for Life-Threatening Illnesses).
2. Friedman J, Polifka J. Teratogenic effects of drugs: a resource for clinicians (TERIS). Baltimore, Maryland: Johns Hopkins University Press, 2000:149-195.
3. Loebstein R, Addis A, Ho E, et al. Pregnancy outcome following gestational exposure to fluoroquinolones: a multicenter prospective controlled study. Antimicrob Agents Chemother. 1998;42(6):1336-1339.
4. Schaefer C, Amoura-Elefant E, Vial T, et al. Pregnancy outcome after prenatal quinolone exposure. Evaluation of a case registry of the European network of teratology information services (ENTIS). Eur J Obstet Gynecol Reprod Biol. 1996;69:83-89.
5. Report presented at the FDA’s Anti-Infective Drug and Dermatological Drug Product’s Advisory Committee meeting, March 31, 1993, Silver Spring, MD. Report available from FDA, CDER, Advisors and Consultants Staff, HFD-21, 1901 Chapman Avenue, Room 200, Rockville, MD 20852, USA.
6. Kelly DJ, et al. Serum concentrations of penicillin, doxycycline, and ciprofloxacin during prolonged therapy in rhesus monkeys. J Infect Dis 1992; 166:1184-7.
7. Friedlander AM, et al. Postexposure prophylaxis against experimental inhalational anthrax. J Infect Dis 1993; 167:1239-42.
8. Anti-infective Drugs Advisory Committee Meeting, April 3, 2012 - The efficacy of Ciprofloxacin for treatment of Pneumonic Plague.

16 HOW SUPPLIED/STORAGE AND HANDLING

CIPRO (ciprofloxacin hydrochloride) Tablets are available as round, slightly yellowish film-coated tablets containing 250 mg ciprofloxacin. The 250 mg tablet is coded with the word “BAYER” on one side and functionally scored and engraved with “CIP 250” on the reverse side. CIPRO is also available as capsule shaped, slightly yellowish film-coated tablets containing 500 mg ciprofloxacin. The 500 mg tablet is coded with the word “BAYER” on one side and functionally scored and engraved with “CIP 500” on the reverse side. CIPRO 250 mg and 500 mg are available in bottles of 100.

 | Strength | NDC Code | Tablet Identification
Bottles of 100: | 250 mg | NDC 50419-758-01 | CIPRO 250
 | 500 mg | NDC 50419-754-01 | CIPRO 500

Store at 20° to 25°C (68° to 77°F); excursions permitted to 15° to 30°C (59° to 86°F) [see USP Controlled Room Temperature].

CIPRO Oral Suspension is supplied in 5% and 10% strengths. The drug product is composed of two components (microcapsules containing the active ingredient and diluent) which must be mixed by the pharmacist [see Dosage and Administration (2.5)].

Strengths | Total volume; after reconstitution | Ciprofloxacin; Concentration | Ciprofloxacin; contents per bottle | NDC Code
5% | 100 mL | 250 mg/5 mL | 5,000 mg | 50419-777-01
10% | 100 mL | 500 mg/5 mL | 10,000 mg | 50419-773-01

Store microcapsules and diluent below 25°C (77°F); excursions are permitted from 15°C to 30°C (59°F to 86°F) [see USP Controlled Room Temperature]. Protect from freezing.

The reconstituted product may be stored at 25°C (77°F) for 14 days; excursions are permitted from 15°C to 30°C (59°F to 86°F) [see USP Controlled Room Temperature]. Protect from freezing.

A graduated teaspoon (5mL) with markings 1/2 (2.5 mL) and 1/1 (5 mL) is provided for the patient.

17 PATIENT COUNSELING INFORMATION

Advise the patient to read the FDA-approved patient labeling (Medication Guide)

Serious Adverse Reactions

Advise patients to stop taking CIPRO if they experience an adverse reaction and to call their healthcare provider for advice on completing the full course of treatment with another antibacterial drug.

Inform patients of the following serious adverse reactions that have been associated with CIPRO or other fluoroquinolone use:

- Disabling and potentially irreversible serious adverse reactions that may occur together: Inform patients that disabling and potentially irreversible serious adverse reactions, including tendinitis and tendon rupture, peripheral neuropathies, and central nervous system effects, have been associated with use of CIPRO and may occur together in the same patient. Inform patients to stop taking CIPRO immediately if they experience an adverse reaction and to call their healthcare provider.
- Tendinitis and tendon rupture: Instruct patients to contact their healthcare provider if they experience pain, swelling, or inflammation of a tendon, or weakness or inability to use one of their joints; rest and refrain from exercise; and discontinue CIPRO treatment. Symptoms may be irreversible. The risk of severe tendon disorder with fluoroquinolones is higher in older patients usually over 60 years of age, in patients taking corticosteroid drugs, and in patients with kidney, heart or lung transplants.
- Peripheral Neuropathies: Inform patients that peripheral neuropathies have been associated with ciprofloxacin use, symptoms may occur soon after initiation of therapy and may be irreversible. If symptoms of peripheral neuropathy including pain, burning, tingling, numbness and/or weakness develop, immediately discontinue CIPRO and tell them to contact their physician.
- Central nervous system effects (for example, convulsions, dizziness, lightheadedness, increased intracranial pressure): Inform patients that convulsions have been reported in patients receiving fluoroquinolones, including Ciprofloxacin. Instruct patients to notify their physician before taking this drug if they have a history of convulsions. Inform patients that they should know how they react to CIPRO before they operate an automobile or machinery or engage in other activities requiring mental alertness and coordination. Instruct patients to notify their physician if persistent headache with or without blurred vision occurs.
- Exacerbation of Myasthenia Gravis: Instruct patients to inform their physician of any history of myasthenia gravis. Instruct patients to notify their physician if they experience any symptoms of muscle weakness, including respiratory difficulties.
- Hypersensitivity Reactions: Inform patients that ciprofloxacin can cause hypersensitivity reactions, even following a single dose, and to discontinue the drug at the first sign of a skin rash, hives or other skin reactions, a rapid heartbeat, difficulty in swallowing or breathing, any swelling suggesting angioedema (for example, swelling of the lips, tongue, face, tightness of the throat, hoarseness), or other symptoms of an allergic reaction.
- Hepatotoxicity: Inform patients that severe hepatotoxicity (including acute hepatitis and fatal events) has been reported in patients taking CIPRO. Instruct patients to inform their physician if they experience any signs or symptoms of liver injury including: loss of appetite, nausea, vomiting, fever, weakness, tiredness, right upper quadrant tenderness, itching, yellowing of the skin and eyes, light colored bowel movements or dark colored urine.
- Aortic aneurysm and dissection: Inform patients to seek emergency medical care if they experience sudden chest, stomach, or back pain.
- Diarrhea: Diarrhea is a common problem caused by antibiotics which usually ends when the antibiotic is discontinued. Sometimes after starting treatment with antibiotics, patients can develop watery and bloody stools (with or without stomach cramps and fever) even as late as two or more months after having taken the last dose of the antibiotic. If this occurs, instruct patients to contact their physician as soon as possible.
- Prolongation of the QT Interval: Instruct patients to inform their physician of any personal or family history of QT prolongation or proarrhythmic conditions such as hypokalemia, bradycardia, or recent myocardial ischemia; if they are taking any Class IA (quinidine, procainamide), or Class III (amiodarone, sotalol) antiarrhythmic agents. Instruct patients to notify their physician if they have any symptoms of prolongation of the QT interval, including prolonged heart palpitations or a loss of consciousness.
- Musculoskeletal Disorders in Pediatric Patients: Instruct parents to inform their child’s physician if the child has a history of joint-related problems before taking this drug. Inform parents of pediatric patients to notify their child’s physician of any joint-related problems that occur during or following ciprofloxacin therapy [see Warnings and Precautions (5.13) and Use in Specific Populations (8.4)].
- Tizanidine: Instruct patients not to use ciprofloxacin if they are already taking tizanidine. CIPRO increases the effects of tizanidine (Zanaflex®).
- Theophylline: Inform patients that ciprofloxacin CIPRO may increase the effects of theophylline. Life-threatening CNS effects and arrhythmias can occur. Advise the patients to immediately seek medical help if they experience seizures, palpitations, or difficulty breathing.
- Caffeine: Inform patients that CIPRO may increase the effects of caffeine. There is a possibility of caffeine accumulation when products containing caffeine are consumed while taking quinolones.
- Photosensitivity/Phototoxicity: Inform patients that photosensitivity/phototoxicity has been reported in patients receiving fluoroquinolones. Inform patients to minimize or avoid exposure to natural or artificial sunlight (tanning beds or UVA/B treatment) while taking quinolones. If patients need to be outdoors while using quinolones, instruct them to wear loose-fitting clothes that protect skin from sun exposure and discuss other sun protection measures with their physician. If a sunburn-like reaction or skin eruption occurs, instruct patients to contact their physician.
- Blood Glucose Disturbances: Inform the patients that if they are diabetic and are being treated with insulin or an oral hypoglycemic agent and a hypoglycemic reaction occurs, they should discontinue CIPRO and consult a physician.
- Lactation: For indications other than inhalational anthrax (post exposure), advise a woman that breastfeeding is not recommended during treatment with Cipro and for an additional 2 days after the last dose. Alternatively, a woman may pump and discard during treatment and for additional 2 days after the last dose [see Use in Specific Populations (8.2)].

Antibacterial Resistance

Inform patients that antibacterial drugs including CIPRO Tablets and CIPRO Oral Suspension should only be used to treat bacterial infections. They do not treat viral infections (for example, the common cold). When CIPRO Tablets and CIPRO Oral Suspension are prescribed to treat a bacterial infection, patients should be told that although it is common to feel better early in the course of therapy, the medication should be taken exactly as directed. Skipping doses or not completing the full course of therapy may (1) decrease the effectiveness of the immediate treatment and (2) increase the likelihood that bacteria will develop resistance and will not be treatable by CIPRO Tablets and CIPRO Oral Suspension or other antibacterial drugs in the future.

Administration Instructions

Instruct the Patient

- To shake CIPRO Oral Suspension vigorously each time before use for approximately 15 seconds.
- To always use the co-packaged graduated measuring spoon with markings for 1/2 (2.5 mL) and 1/1 (5 mL), to obtain the exact dose.
- After use, the graduated measuring spoon should be cleaned under running water with dish detergent and dried thoroughly.
- Not to chew the microcapsules, but to swallow them whole.
- That water may be taken afterwards.
- Reclose the bottle properly after each use according to instructions on the cap.
- After treatment has been completed, CIPRO Oral Suspension should not be reused.

Inform patients that CIPRO may be taken with or without food.

Inform patients to drink fluids liberally while taking CIPRO to avoid formation of highly concentrated urine and crystal formation in the urine.

Inform patients that antacids containing magnesium, or aluminum, as well as sucralfate, metal cations such as iron, and multivitamin preparations with zinc or didanosine should be taken at least two hours before or six hours after CIPRO administration. CIPRO should not be taken with dairy products (like milk or yogurt) or calcium-fortified juices alone since absorption of ciprofloxacin may be significantly reduced; however, CIPRO may be taken with a meal that contains these products.

Advise patients that if a dose is missed, it should be taken anytime but not later than 6 hours prior to the next scheduled dose. If less than 6 hours remain before the next dose, the missed dose should not be taken and treatment should be continued as prescribed with the next scheduled dose. Double doses should not be taken to compensate for a missed dose.

Advise patients that CIPRO Tablets (250 mg and 500 mg) are scored and can be split into one-half at the scored line to provide a 125 mg or 250 mg strength, respectively.

Drug Interactions Oral Antidiabetic Agents

Inform patients that hypoglycemia has been reported when ciprofloxacin and oral antidiabetic agents were co-administered; if low blood sugar occurs with CIPRO, instruct them to consult their physician and that their antibacterial medicine may need to be changed.

Anthrax and Plague Studies

Inform patients given CIPRO for these conditions that efficacy studies could not be conducted in humans for feasibility reasons. Therefore, approval for these conditions was based on efficacy studies conducted in animals.

Medication Guide

CIPRO® (Sip-row)

(ciprofloxacin hydrochloride)

tablets, for oral use

CIPRO® (Sip-row)

(ciprofloxacin)

for oral suspension

Read this Medication Guide before you start taking CIPRO and each time you get a refill. There may be new information. This information does not take the place of talking to your healthcare provider about your medical condition or your treatment.

What is the most important information I should know about CIPRO?

CIPRO, a fluoroquinolone antibacterial medicine, can cause serious side effects. Some of these serious side effects can happen at the same time and could result in death.

If you get any of the following serious side effects while you take CIPRO, you should stop taking CIPRO immediately and get medical help right away.

1. Tendon rupture or swelling of the tendon (tendinitis).
2. Tendon problems can happen in people of all ages who take CIPRO. Tendons are tough cords of tissue that connect muscles to bones. Symptoms of tendon problems may include:
3. pain
4. swelling
5. tears and swelling of the tendons including the back of the ankle (Achilles), shoulder, hand, thumb, or other tendon sites.
6. The risk of getting tendon problems while you take CIPRO is higher if you:
7. are over 60 years of age
8. are taking steroids (corticosteroids)
9. have had a kidney, heart or lung transplant.
10. Tendon problems can happen in people who do not have the above risk factors when they take CIPRO.
11. Other reasons that can increase your risk of tendon problems can include:
12. physical activity or exercise
13. kidney failure
14. tendon problems in the past, such as in people with rheumatoid arthritis (RA).
15. Stop taking CIPRO immediately and get medical help right away at the first sign of tendon pain, swelling or inflammation. The most common area of pain and swelling is the Achilles tendon at the back of your ankle. This can also happen with other tendons.
16. Tendon rupture can happen while you are taking or after you have finished taking CIPRO. Tendon ruptures can happen within hours or days of taking CIPRO and have happened up to several months after people have finished taking their fluoroquinolone.
17. Stop taking CIPRO immediately and get medical help right away if you get any of the following signs or symptoms of a tendon rupture:
18. hear or feel a snap or pop in a tendon area
19. bruising right after an injury in a tendon area
20. unable to move the affected area or bear weight
The tendon problems may be permanent.
2. Changes in sensation and possible nerve damage (Peripheral Neuropathy). Damage to the nerves in arms, hands, legs, or feet can happen in people who take fluoroquinolones, including CIPRO. Stop taking CIPRO immediately and talk to your healthcare provider right away if you get any of the following symptoms of peripheral neuropathy in your arms, hands, legs, or feet:

- pain
- burning
- tingling

- numbness
- weakness

CIPRO may need to be stopped to prevent permanent nerve damage.

3. Central Nervous System (CNS) effects. Mental health problems and seizures have been reported in people who take fluoroquinolone antibacterial medicines, including CIPRO. Tell your healthcare provider if you have a history of seizures before you start taking CIPRO. CNS side effects may happen as soon as after taking the first dose of CIPRO. Stop taking CIPRO immediately and talk to your healthcare provider right away if you get any of these side effects, or other changes in mood or behavior:

- Seizures
- Hear voices, see things, or sense things that are not there (hallucinations)
- Feel agitated
- Tremors
- Feel anxious or nervous
- Confusion
- Depression
- Reduced awareness of surroundings

- Trouble sleeping
- Nightmares
- Feel lightheaded or dizzy
- Feel more suspicious (paranoia)
- Suicidal thoughts or acts
- Headaches that will not go away, with or without blurred vision
- Memory problems
- False or strange thoughts or beliefs (delusions)

These changes may be permanent.

4. Worsening of myasthenia gravis (a problem that causes muscle weakness). Fluoroquinolones like CIPRO may cause worsening of myasthenia gravis symptoms, including muscle weakness and breathing problems. Tell your healthcare provider if you have a history of myasthenia gravis before you start taking CIPRO. Call your healthcare provider right away if you have any worsening muscle weakness or breathing

What is CIPRO?

CIPRO is a fluoroquinolone antibacterial medicine used in adults age 18 years and older to treat certain infections caused by certain germs called bacteria. These bacterial infections include:

- urinary tract infection

- bone and joint infection

- cervical and urethral gonorrhea, uncomplicated

- chronic prostate infection

- nosocomial pneumonia

- people with a low white blood cell count and a fever

- lower respiratory tract infection

- intra-abdominal infection, complicated

- inhalational anthrax

- sinus infection

- infectious diarrhea

- plague

- skin infection

- typhoid (enteric) fever

- Studies of CIPRO for use in the treatment of plague and anthrax were done in animals only, because plague and anthrax could not be studied in people.
- CIPRO should not be used in people with acute exacerbation of chronic bronchitis, acute uncomplicated cystitis, and sinus infections, if there are other treatment options available.
- CIPRO should not be used as the first choice of antibacterial medicine to treat lower respiratory tract infections caused by a certain type of bacterial called Streptococcus pneumoniae.
- CIPRO is also used in children younger than 18 years of age to treat complicated urinary tract and kidney infections or who may have breathed in anthrax germs, have plague or have been exposed to plague germs.
- Children younger than 18 years of age have a higher chance of getting bone, joint, or tendon (musculoskeletal) problems such as pain or swelling while taking CIPRO. CIPRO should not be used as the first choice of antibacterial medicine in children under 18 years of age.

Who should not take CIPRO?

Do not take CIPRO if you:

- have ever had a severe allergic reaction to an antibacterial medicine known as a fluoroquinolone, or are allergic to ciprofloxacin hydrochloride or any of the ingredients in CIPRO. See the end of this Medication Guide for a complete list of ingredients in CIPRO.
- also take a medicine called tizanidine (Zanaflex®).

Ask your healthcare provider if you are not sure.

What should I tell my healthcare provider before taking CIPRO?

Before you take CIPRO, tell your healthcare provider about all your medical conditions, including if you:

- have tendon problems. CIPRO should not be used in people who have a history of tendon problems.
- have a disease that causes muscle weakness (myasthenia gravis). CIPRO should not be used in people who have a known history of myasthenia gravis.
- have liver problems.
- have central nervous system problems (such as epilepsy).
- have nerve problems. CIPRO should not be used in people who have a history of a nerve problem called peripheral neuropathy have or anyone in your family has an irregular heartbeat, or heart attack, especially a condition called “QT prolongation”.
- have low blood potassium (hypokalemia) or low magnesium (hypomagnesemia).
- have or have had seizures.
- have kidney problems. You may need a lower dose of CIPRO if your kidneys do not work well.
- have diabetes or problems with low blood sugar (hypoglycemia).
- have joint problems including rheumatoid arthritis (RA).
- have trouble swallowing pills.
- are pregnant or plan to become pregnant. It is not known if CIPRO will harm your unborn baby.
- are breastfeeding or plan to breastfeed. CIPRO passes into your breast milk.
  - You should not breastfeed during treatment with CIPRO and for 2 days after taking your last dose of CIPRO. You may pump your breast milk and throw it away during treatment with CIPRO and for 2 days after taking your last dose of CIPRO.
  - If you are taking CIPRO for inhalation anthrax, you and your healthcare provider should decide whether you can continue breastfeeding while taking CIPRO.

Tell your healthcare provider about all the medicines you take, including prescription and over-the-counter medicines, vitamins, and herbal supplements.

- CIPRO and other medicines can affect each other causing side effects.
- Especially tell your healthcare provider if you take:
- a steroid medicine.
- an anti-psychotic medicine.
- a tricyclic antidepressant.
- a water pill (diuretic).
- theophylline (such as Theo-24®, Elixophyllin®, Theochron®, Uniphyl®, Theolair®).
- a medicine to control your heart rate or rhythm (antiarrhythmics).
- an oral anti-diabetes medicine.
- phenytoin (Fosphenytoin Sodium®, Cerebyx®, Dilantin-125®, Dilantin®, Extended Phenytoin Sodium®, Prompt Phenytoin Sodium®, Phenytek®).
- cyclosporine (Gengraf®, Neoral®, Sandimmune®, Sangcya®).
- a blood thinner (such as warfarin, Coumadin®, Jantoven®).
- methotrexate (Trexall®).
- ropinirole (Requip®).
- clozapine (Clozaril®, Fazaclo® ODT®).
- a Non-Steroidal Anti-Inflammatory Drug (NSAID). Many common medicines for pain relief are NSAIDs. Taking an NSAID while you take CIPRO or other fluoroquinolones may increase your risk of central nervous system effects and seizures.
- sildenafil (Viagra®, Revatio®).
- duloxetine.
- products that contain caffeine.
- probenecid (Probalan®, Col-probenecid ®).
- Certain medicines may keep CIPRO Tablets and CIPRO Oral Suspension from working correctly. Take CIPRO Tablets and Oral Suspension either 2 hours before or 6 hours after taking these medicines, vitamins, or supplements:
- an antacid, multivitamin, or other medicine or supplements that has magnesium, calcium, aluminum, iron, or zinc.
- sucralfate (Carafate®).
- didanosine (Videx®, Videx EC®).

Ask your healthcare provider for a list of these medicines if you are not sure.

Know the medicines you take. Keep a list of them to show your healthcare provider and pharmacist when you get a new medicine.

How should I take CIPRO?

- Take CIPRO exactly as your healthcare provider tells you to take it.
- Your healthcare provider will tell you how much CIPRO to take and when to take it.
- CIPRO can be taken with or without food.
- CIPRO should not be taken with dairy products (like milk or yogurt) or calcium-fortified juices alone but may be taken with a meal that contains these products.
- Drink plenty of fluids while taking CIPRO.
- Do not skip any doses of CIPRO, or stop taking it, even if you begin to feel better, until you finish your prescribed treatment unless:
  - you have tendon problems. See “What is the most important information I should know about CIPRO?”
  - you have nerve problems. See “What is the most important information I should know about CIPRO?”
  - you have central nervous system problems. See “What is the most important information I should know about CIPRO?”
  - you have a serious allergic reaction. See “What are the possible side effects of CIPRO?”
  - your healthcare provider tells you to stop taking CIPRO.
Taking all of your CIPRO doses will help make sure that all of the bacteria are killed. Taking all of your CIPRO doses will help lower the chance that the bacteria will become resistant to CIPRO. If you become resistant to CIPRO, CIPRO and other antibacterial medicines may not work for you in the future.
- If you take too much CIPRO, call your healthcare provider or get medical help right away.
- CIPRO is supplied as a scored tablet (CIPRO Tablets), oral suspension (CIPRO Oral Suspension), extended-release tablet (CIPRO XR) and injection for intravenous infusion (CIPRO IV). Read and follow the instructions below for the type of CIPRO your healthcare provider has prescribed for you.

CIPRO Tablets:

- CIPRO Tablets comes as 250 mg and 500 mg scored tablets that can be taken whole or may be broken in half at the scored line. Your healthcare provider will tell you how much CIPRO Tablets to take and if you will need to break CIPRO Tablets in half to get your prescribed dose.
- Take CIPRO Tablets in the morning and evening at about the same time each day. Do not crush or chew the tablet. Tell your healthcare provider if you cannot swallow the tablet.
- If you miss a dose of CIPRO Tablets and it is:
  - 6 hours or more until your next scheduled dose, take your missed dose right away. Then take the next dose at your regular time.
  - less than 6 hours until your next scheduled dose, do not take the missed dose. Take the next dose at your regular time.
- Do not take 2 doses of CIPRO Tablets at 1 time to make up for a missed dose. If you are not sure about when to take CIPRO Tablets after a missed dose, ask your healthcare provider or pharmacist.

CIPRO Oral Suspension:

- Take CIPRO Oral Suspension in the morning and evening at about the same time each day. Shake the CIPRO Oral Suspension bottle well each time before use for about 15 seconds to make sure the suspension is mixed well. Close the bottle completely after use.
- If you miss a dose of CIPRO Oral Suspension and it is:
  - 6 hours or more until your next scheduled dose, take your missed dose right away. Then take the next dose at your regular time.
  - less than 6 hours until your next scheduled dose, do not take the missed dose. Take the next dose at your regular time.
- Do not take 2 doses of CIPRO Oral Suspension at 1 time to make up for a missed dose. If you are not sure about when to take CIPRO Oral Suspension after a missed dose, ask your healthcare provider or pharmacist.

What should I avoid while taking CIPRO?

- CIPRO can make you feel dizzy and lightheaded. Do not drive, operate machinery, or do other activities that require mental alertness or coordination until you know how CIPRO affects you.
- Avoid sunlamps, tanning beds, and try to limit your time in the sun. CIPRO can make your skin sensitive to the sun (photosensitivity) and the light from sunlamps and tanning beds. You could get a severe sunburn, blisters or swelling of your skin. If you get any of these symptoms while you take CIPRO, call your healthcare provider right away. You should use a sunscreen and wear a hat and clothes that cover your skin if you have to be in sunlight.

What are the possible side effects of CIPRO?

CIPRO may cause serious side effects, including:

- See “What is the most important information I should know about CIPRO?”
- Serious allergic reactions. Serious allergic reactions, including death, can happen in people taking fluoroquinolones, including CIPRO, even after only 1 dose. Stop taking CIPRO and get emergency medical help right away if you get any of the following symptoms of a severe allergic reaction:

Skin rash may happen in people taking CIPRO even after only 1 dose. Stop taking CIPRO at the first sign of a skin rash and call your healthcare provider. Skin rash may be a sign of a more serious reaction to CIPRO.
2. Liver damage (hepatotoxicity). Hepatotoxicity can happen in people who take CIPRO. Call your healthcare provider right away if you have unexplained symptoms such as:

1. Aortic aneurysm and dissection. Tell your healthcare provider if you have ever been told that you have an aortic aneurysm, a swelling of the large artery that carries blood from the heart to the body. Get emergency medical help right away if you have sudden chest, stomach, or back pain.
2. Intestine infection (Clostridioides difficile – associated diarrhea). Clostridioides difficile-associated diarrhea (CDAD) can happen with many antibacterial medicines, including CIPRO. Call your healthcare provider right away if you get watery diarrhea, diarrhea that does not go away, or bloody stools. You may have stomach cramps and a fever. CDAD can happen 2 or more months after you have finished your antibacterial medicine.
3. Serious heart rhythm changes (QT prolongation and torsade de pointes). Tell your healthcare provider right away if you have a change in your heartbeat (a fast or irregular heartbeat), or if you faint. CIPRO may cause a rare heart problem known as prolongation of the QT interval. This condition can cause an abnormal heartbeat and can be very dangerous. The chances of this event are higher in people:
  - who are elderly.
  - with a family history of prolonged QT interval.
  - with low blood potassium (hypokalemia) or low magnesium (hypomagnesemia).
  - who take certain medicines to control heart rhythm (antiarrhythmics).
4. Joint Problems. Increased chance of problems with joints and tissues around joints in children under 18 years old can happen. Tell your child’s healthcare provider if your child has any joint problems during or after treatment with CIPRO.
5. Sensitivity to sunlight (photosensitivity). See “What should I avoid while taking CIPRO?”
6. Changes in blood sugar. People who take CIPRO and other fluoroquinolone medicines with oral anti-diabetes medicines or with insulin can get low blood sugar (hypoglycemia) and high blood sugar (hyperglycemia). Follow your healthcare provider's instructions for how often to check your blood sugar. If you have diabetes and you get low blood sugar while taking CIPRO, stop taking CIPRO and call your healthcare provider right away. Your antibiotic medicine may need to be changed.

The most common side effects of CIPRO include:

- nausea
- diarrhea
- changes in liver function tests
- vomiting
- rash

Tell your healthcare provider about any side effect that bothers you or that does not go away.

These are not all the possible side effects of CIPRO. For more information, ask your healthcare provider or pharmacist.

Call your doctor for medical advice about side effects. You may report side effects to FDA at 1-800-FDA-1088.

How should I store CIPRO?

CIPRO Tablets

- Store at room temperature between 68°F to 77°F (20°C to 25°C).

CIPRO Oral Suspension

- Store microcapsules and diluent at room temperature up to 77°F (25°C).
- Do not freeze.
- After your CIPRO treatment is finished, safely throw away any unused oral suspension.

Keep CIPRO and all medicines out of the reach of children.

General Information about the safe and effective use of CIPRO.

Medicines are sometimes prescribed for purposes other than those listed in a Medication Guide. Do not use CIPRO for a condition for which it is not prescribed. Do not give CIPRO to other people, even if they have the same symptoms that you have. It may harm them.

This Medication Guide summarizes the most important information about CIPRO. If you would like more information about CIPRO, talk with your healthcare provider. You can ask your healthcare provider or pharmacist for information about CIPRO that is written for health professionals.

What are the ingredients in CIPRO?

CIPRO Tablets:

- Active ingredient: ciprofloxacin hydrochloride
- Inactive ingredients: cornstarch, crospovidone, hypromellose, magnesium stearate, microcrystalline cellulose, polyethylene glycol, silicon dioxide, and titanium dioxide.

CIPRO Oral Suspension:

- Active ingredient: ciprofloxacin
- Inactive ingredients:
- Microcapsules contains: hypromellose, magnesium stearate, methacrylic acid copolymer, and Polysorbate 20 and povidone.
- Diluent contains: medium-chain triglycerides, sucrose, soy-lecithin, water, and strawberry flavor.

Manufactured for:

Bayer HealthCare Pharmaceuticals Inc.

Whippany, NJ 07981

CIPRO is a registered trademark of Bayer Aktiengesellschaft.

Rx Only

©1987 Bayer HealthCare Pharmaceuticals Inc.

For more information, call 1-1-888-842-2937.

This Medication Guide has been approved by the U.S. Food and Drug Administration Revised: 11/2021

PACKAGE/LABEL PRINCIPAL DISPLAY PANEL

Cipro 250 mg 100 Tablets

NDC 50419-758-01

Cipro®

(ciprofloxacin hydrochloride)

Equivalent to

250 mg ciprofloxacin

100 Tablets Rx Only

Attention Pharmacist:

Dispense the enclosed Medication Guide

to each patient.

Manufactured by:

Bayer HealthCare Pharmaceuticals Inc.

Whippany, NJ 07981

Manufactured in Germany

PACKAGE/LABEL PRINCIPAL DISPLAY PANEL

Cipro 500 mg 100 Tablets

NDC 50419-754-01

Cipro®

(ciprofloxacin hydrochloride)

Equivalent to

500 mg ciprofloxacin

100 Tablets Rx Only

Attention Pharmacist:

Dispense the enclosed Medication Guide

to each patient.

Manufactured by:

Bayer HealthCare Pharmaceuticals Inc.

Whippany, NJ 07981

Manufactured in Germany

PACKAGE/LABEL PRINCIPAL DISPLAY PANEL

Cipro® 5% Oral Suspension Kit

NDC 50419-777-01

Cipro 5% Oral Suspension

FOR ORAL USE ONLY

5 g/100 mL

250 mg ciprofloxacin/5 mL

Ciprofloxacin Oral Suspension 5 g/100 mLconsists of the following components:

- 1 bottle consists of microcapsules which contain 5 g ciprofloxacin
- 1 bottle with suspension diluent to prepare100 mL of ciprofloxacin suspension 5%
- 1 graduated (5 mL) spoon (Product of Germany)

Attention Pharmacist: Dispense the enclosed Medication Guide to each patient Rx Only

Manufactured for:

Bayer HealthCare Pharmaceuticals Inc.

Whippany, NJ 07981

Manufactured in Italy

PACKAGE/LABEL PRINCIPAL DISPLAY PANEL

NDC 50419-773-01

Cipro 10% Oral Suspension

FOR ORAL USE ONLY

10 g/100 mL

500 mg ciprofloxacin/5 mL

Ciprofloxacin Oral Suspension 10 g/100 mLconsists of the following components:

- 1 bottle consists of microcapsules which contain 10 g ciprofloxacin
- 1 bottle with suspension diluent to prepare100 mL of ciprofloxacin suspension 10%
- 1 graduated (5 mL) spoon (Product of Germany)

Attention Pharmacist: Dispense the enclosed Medication Guide to each patient Rx Only

Manufactured for:

Bayer HealthCare Pharmaceuticals Inc.

Whippany, NJ 07981

Manufactured in Italy